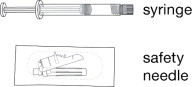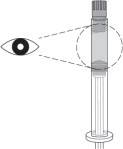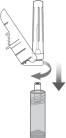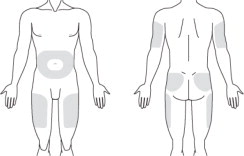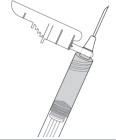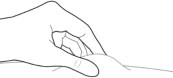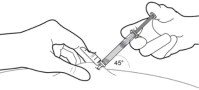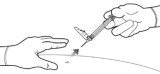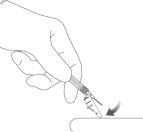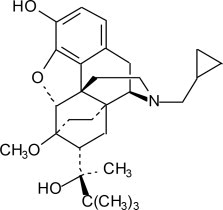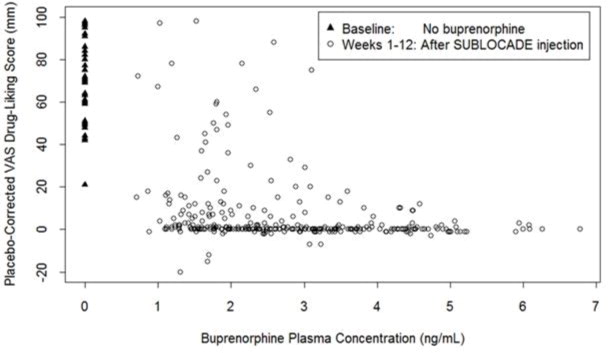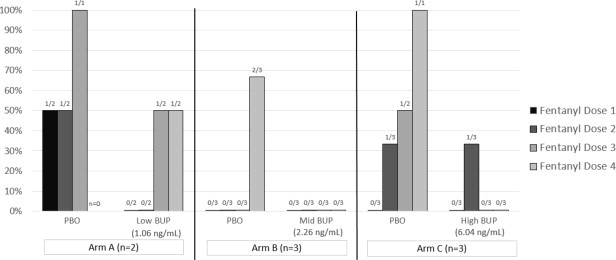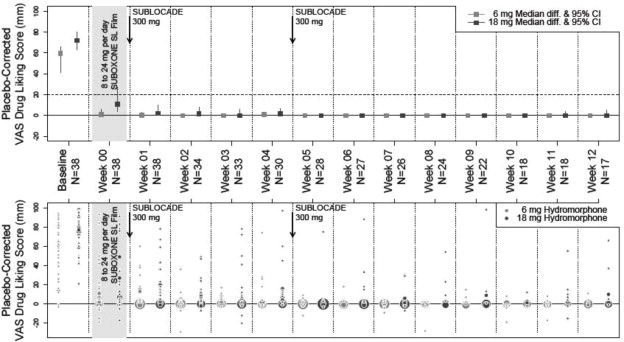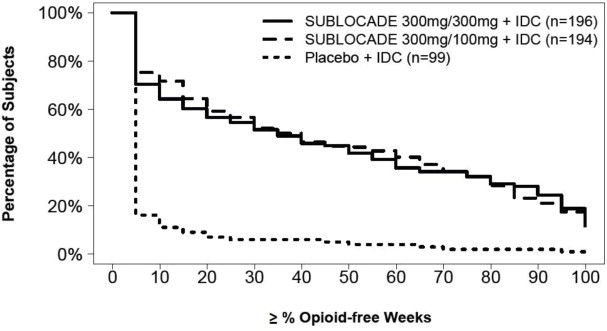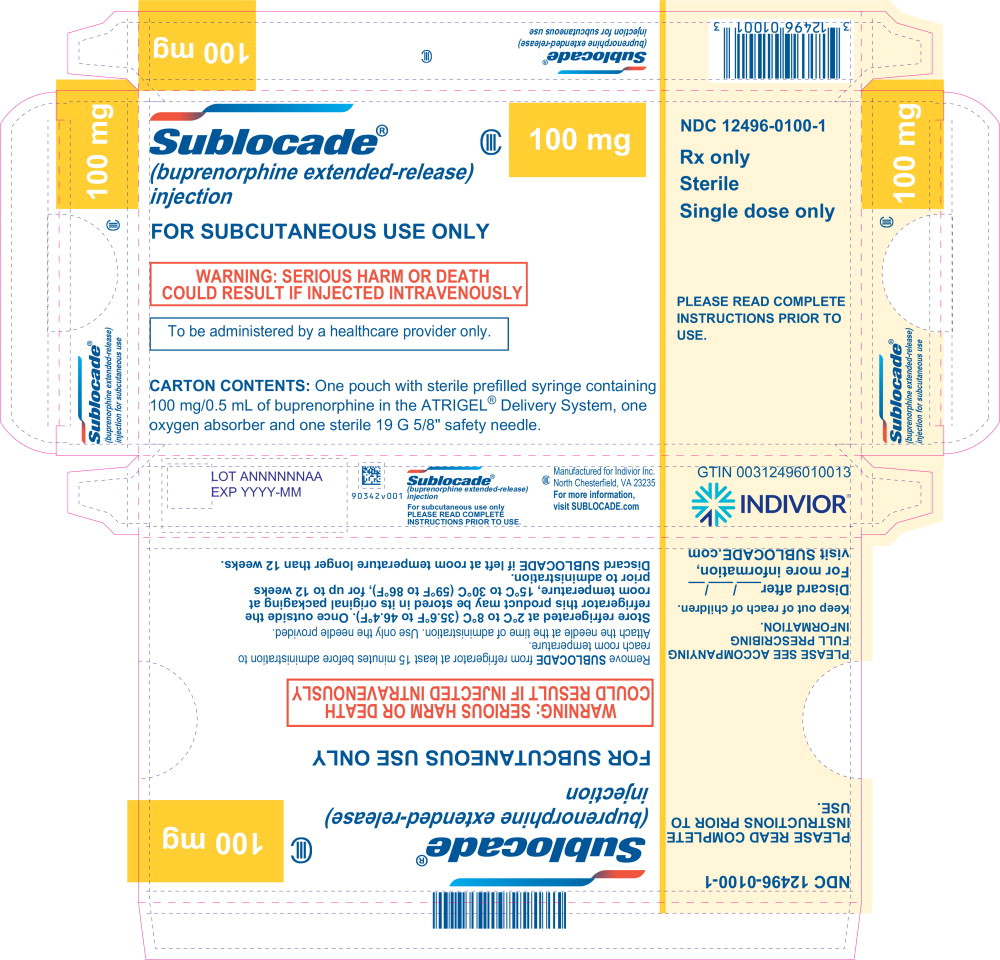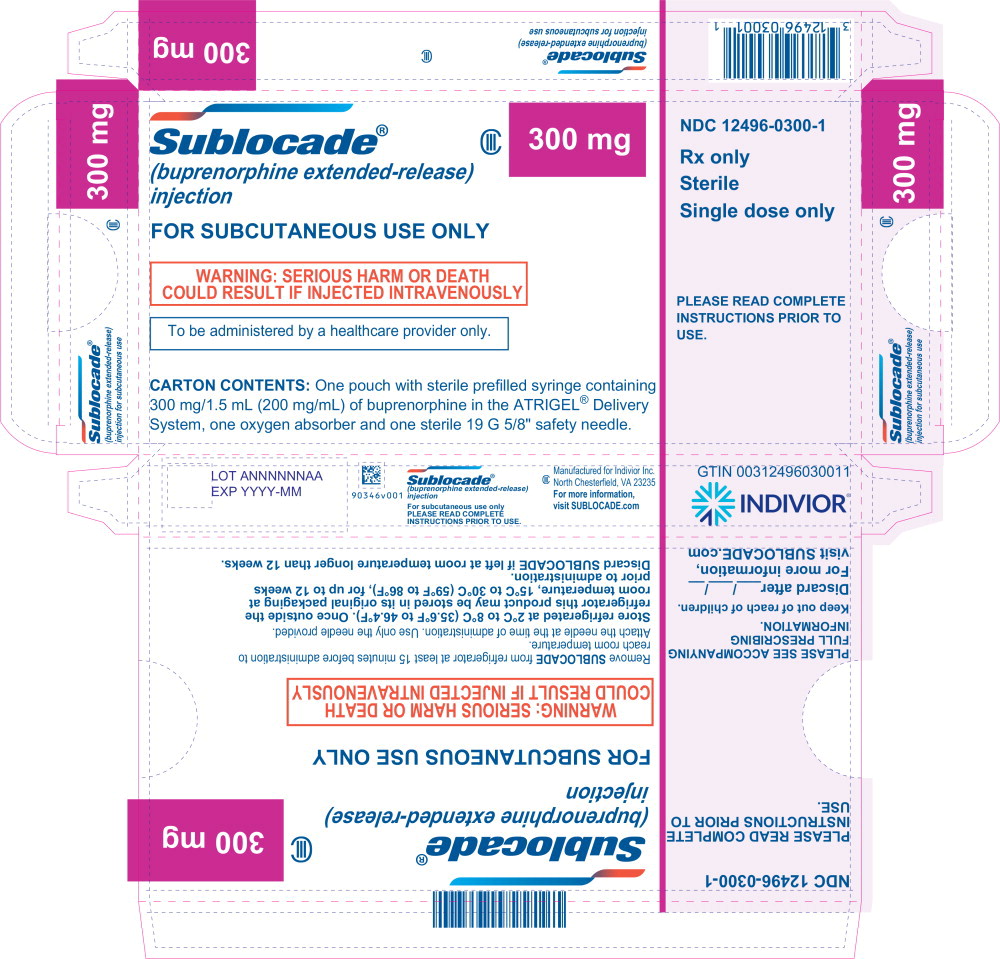 DRUG LABEL: SUBLOCADE

NDC: 12496-0100 | Form: SOLUTION
Manufacturer: Indivior Inc.
Category: prescription | Type: HUMAN PRESCRIPTION DRUG LABEL
Date: 20251222
DEA Schedule: CIII

ACTIVE INGREDIENTS: BUPRENORPHINE
 100 mg/1 1
INACTIVE INGREDIENTS: POLY(DL-LACTIC-CO-GLYCOLIC ACID), (50:50; 15000 MW); METHYLPYRROLIDONE

HIGHLIGHTS OF PRESCRIBING INFORMATION

These highlights do not include all the information needed to use SUBLOCADE®safely and effectively. See full prescribing information for SUBLOCADE.
SUBLOCADE (buprenorphine extended-release) injection, for subcutaneous use, CIII
Initial U.S. Approval: 2002

RECENT MAJOR CHANGES

Indications and Usage (1) | 02/2025
Dosage and Administration (2.1, 2.3, 2.5) | 02/2025
Dosage and Administration (2.2) | 12/2025
Warnings and Precautions (5.4, 5.5) | 12/2025
Warnings and Precautions (5.12) | 02/2025

WARNING: RISK OF SERIOUS HARM OR DEATH WITH INTRAVENOUS ADMINISTRATION; SUBLOCADE RISK EVALUATION AND MITIGATION STRATEGY

See full prescribing information for complete boxed warning.

- Serious harm or death could result if administered intravenously. (5.1)
- SUBLOCADE is only available through a restricted program called the SUBLOCADE REMS Program. Healthcare settings and pharmacies that order and dispense SUBLOCADE must be certified in this program and comply with the REMS requirements. (5.2)

1 INDICATIONS AND USAGE

SUBLOCADE contains buprenorphine, a partial opioid agonist, and is indicated for the treatment of moderate to severe opioid use disorder in patients who have initiated treatment with a single dose of a transmucosal buprenorphine product or who are already being treated with buprenorphine. (1)

SUBLOCADE should be used as part of a complete treatment program that includes counseling and psychosocial support. (1)

2 DOSAGE AND ADMINISTRATION

SUBLOCADE is for healthcare provider preparation and administration only. (2.1)

SUBLOCADE is administered only by subcutaneous injection in the abdomen, thigh, buttock, or back of the upper arm. (2.1)

Strongly consider recommending or prescribing an opioid overdose reversal agent (e.g., naloxone, nalmefene) at the time SUBLOCADE is initiated or renewed because patients being treated for opioid use disorder have the potential for relapse, putting them at risk for opioid overdose. (2.2)

Patients not currently taking buprenorphine should receive an initial dose (e.g. 4 mg) of transmucosal buprenorphine before administering the first injection of SUBLOCADE. Monitor patients in a healthcare setting after injection with SUBLOCADE to assess for symptoms of worsening withdrawal or sedation. Patients' symptoms should be stable or improving prior to release from the healthcare setting. (2.3)

The second injection of SUBLOCADE may be administered as early as one week after the first injection. (2.3)

Injection sites should be rotated between doses. (2.3)

The recommended dose of SUBLOCADE is two initial doses of 300 mg followed by 100 mg monthly maintenance doses. (2.3)

Increasing the maintenance dose to 300 mg monthly may be considered for patients in which the benefits outweigh the risks. (2.3)

Examine the injection site for signs of infection or evidence of tampering or attempts to remove the depot. (2.4)

See Full Prescribing Information for administration instructions. (2.5)

3 DOSAGE FORMS AND STRENGTHS

Injection: 100 mg/0.5 mL and 300 mg/1.5 mL provided in a prefilled, single-dose syringe with a 19 Gauge 5/8-inch needle. (3)

4 CONTRAINDICATIONS

Hypersensitivity to buprenorphine or any other ingredients in SUBLOCADE. (4)

5 WARNINGS AND PRECAUTIONS

Addiction, Abuse, and Misuse: Buprenorphine can be abused in a manner similar to other opioids. Monitor patients for conditions indicative of diversion or progression of opioid dependence and addictive behaviors. (5.3)

Respiratory Depression: Life-threatening respiratory depression and death have occurred in association with buprenorphine. Warn patients of the potential danger of self-administration of benzodiazepines or other CNS depressants while under treatment with SUBLOCADE. (5.4, 5.5)

Risk of Serious Injection Site Reactions: Likelihood may be increased with inadvertent intramuscular or intradermal administration. Evaluate and treat as appropriate. (5.6).

Neonatal Opioid Withdrawal Syndrome: Neonatal opioid withdrawal syndrome (NOWS) is an expected and treatable outcome of prolonged use of opioids during pregnancy. (5.7)

Adrenal Insufficiency: If diagnosed, treat with physiologic replacement of corticosteroids, and wean patient off of the opioid. (5.8)

Risk of Opioid Withdrawal With Abrupt Discontinuation: If treatment with SUBLOCADE is discontinued, monitor patients for several months for withdrawal and treat appropriately. (5.9)

Risk of Hepatitis, Hepatic Events: Monitor liver function tests prior to and during treatment. (5.10)

Risk of Withdrawal in Patients Dependent on Full Agonist Opioids:

Verify that patients have tolerated transmucosal buprenorphine before injecting SUBLOCADE. (5.12)

Treatment of Emergent Acute Pain: Treat pain with a non-opioid analgesic whenever possible. If opioid therapy is required, monitor patients closely because higher doses may be required for analgesic effect. (5.13)

6 ADVERSE REACTIONS

Adverse reactions commonly associated with SUBLOCADE (in ≥ 5% of subjects) were constipation, headache, nausea, injection site pruritus, vomiting, increased hepatic enzymes, fatigue, and injection site pain. (6)

To report SUSPECTED ADVERSE REACTIONS, contact Indivior Inc. at 1-877-782-6966 or FDA at 1-800-FDA-1088 or www.fda.gov/medwatch.

7 DRUG INTERACTIONS

CYP3A4 Inhibitors and Inducers: Monitor patients starting or ending CYP3A4 inhibitors or inducers for potential over- or under-dosing. (7)

Serotonergic Drugs: If concomitant use is warranted, monitor for serotonin syndrome, particularly during treatment initiation, and during dose adjustment of the serotonergic drug. (7)

8 USE IN SPECIFIC POPULATIONS

Lactation: Buprenorphine passes into the mother's milk. (8.2)

Geriatric Patients: Monitor for sedation or respiratory depression. (8.5)

Moderate to Severe Hepatic Impairment: Not recommended. (5.15, 8.6)

FULL PRESCRIBING INFORMATION

WARNING: RISK OF SERIOUS HARM OR DEATH WITH INTRAVENOUS ADMINISTRATION; SUBLOCADE RISK EVALUATION AND MITIGATION STRATEGY

- Serious harm or death could result if administered intravenously. SUBLOCADE forms a solid mass upon contact with body fluids and may cause occlusion, local tissue damage, and thrombo-embolic events, including life threatening pulmonary emboli, if administered intravenously. (5.1)
- Because of the risk of serious harm or death that could result from intravenous self-administration, SUBLOCADE is only available through a restricted program called the SUBLOCADE REMS Program. Healthcare settings and pharmacies that order and dispense SUBLOCADE must be certified in this program and comply with the REMS requirements. (5.2)

1 INDICATIONS AND USAGE

SUBLOCADE is indicated for the treatment of moderate to severe opioid use disorder in patients who have initiated treatment with a single dose of a transmucosal buprenorphine product or who are already being treated with buprenorphine.

SUBLOCADE should be used as part of a complete treatment plan that includes counseling and psychosocial support.

2 DOSAGE AND ADMINISTRATION

2.1 Important Dosing and Administration Information

FOR SUBCUTANEOUS INJECTION ONLY. DO NOT ADMINISTER SUBLOCADE INTRAVENOUSLY, INTRAMUSCULARLY OR INTRADERMALLY [see Dosage and Administration (2.5), Warnings and Precautions (5.1, 5.6)] .

- SUBLOCADE is for healthcare provider preparation and administration only.
- SUBLOCADE must be injected into the subcutaneous tissue of the abdomen, thigh, buttock, or back of the upper arm.
- Patients not currently taking buprenorphine should receive an initial dose (e.g. 4 mg) of transmucosal buprenorphine before administering the first injection of SUBLOCADE. Monitor patients in a healthcare setting after injection with SUBLOCADE to assess for symptoms of worsening withdrawal or sedation. Patients' symptoms should be stable or improving prior to release from the healthcare setting.
- The second injection of SUBLOCADE may be administered as early as one week after the first injection.
- Injection sites should be rotated between doses.
- Administer maintenance injections at least 26 days apart.
- A patient who misses a maintenance dose should receive the next dose as soon as possible.
- Administer each injection only using the syringe and safety needle included with the product [see Dosage and Administration (2.5)] .

2.2 Patient Access to an Opioid Overdose Reversal Agent for the Emergency Treatment of Opioid Overdose

Inform patients and caregivers about opioid overdose reversal agents (e.g., naloxone, nalmefene) and discuss the importance of having access to an opioid overdose reversal agent. Because patients being treated for opioid use disorder have the potential for relapse, putting them at risk for opioid overdose, strongly consider recommending or prescribing an overdose reversal agent for the emergency treatment of opioid overdose, both when initiating and renewing treatment with SUBLOCADE. Also consider recommending or prescribing such an agent if the patient has household members (including children) or other close contacts at risk for accidental ingestion or opioid overdose [see Warnings and Precautions (5.4)] .

Discuss the options for obtaining an opioid overdose reversal agent (e.g., prescription, over-the-counter, or as part of a community-based program) [see Warning and Precautions (5.4)].

There are important differences among the opioid overdose reversal agents, such as route of administration, product strength, approved patient age range, and pharmacokinetics. Be familiar with these differences, as outlined in the approved labeling for those products, prior to recommending or prescribing such an agent.

Advise patients and caregivers that opioid overdose reversal agents, such as naloxone or nalmefene, may also be administered for a known or suspected overdose with buprenorphine itself. Higher than normal doses and repeated administration of an opioid overdose reversal agent may be necessary due to the long duration of action of buprenorphine and its affinity for the mu-opioid receptor [see Overdosage (10)] .

2.3 Recommended Dosage

Induction in patients not already receiving buprenorphine

Treatment with buprenorphine should be initiated when objective and clear signs of opioid withdrawal are evident in order to minimize the risk of precipitating withdrawal [see Warnings and Precautions (5.12)] .

Patients should receive an initial dose (e.g. 4 mg) of transmucosal buprenorphine and be observed for one hour to confirm tolerability before administering the first injection of SUBLOCADE. The recommended starting dose of SUBLOCADE is 300 mg. Monitor patients in a healthcare setting after injection with SUBLOCADE to assess for symptoms of worsening withdrawal or sedation. Patients' symptoms should be stable or improving prior to release from the healthcare setting. On induction day, up to an additional 8 mg of transmucosal buprenorphine could be administered to manage withdrawal symptoms.

The recommended dose for the second injection is 300 mg. The second injection may be administered as early as 1 week and up to 1 month after the initial injection, based on patient need [ see Table 1].

Transition of patients already receiving transmucosal buprenorphine

Patients who have been on 8 mg to 24 mg daily of transmucosal buprenorphine may be transitioned directly to the recommended starting dose of 300 mg of SUBLOCADE. The recommended dose for the second injection is 300 mg. The second injection may be administered as early as 1 week and up to 1 month after the initial injection, based on patient need [ see Table 1].

Patients established on long-term treatment and whose symptoms are controlled with 8 mg to 18 mg daily of transmucosal buprenorphine may receive 100 mg of SUBLOCADE as their second dose if symptoms remain controlled following the initial dose of 300 mg [ see Table 1].

Maintenance dosage

After the first two injections, the recommended maintenance dosage of SUBLOCADE is 100 mg monthly. A monthly maintenance dosage of 300 mg may be considered in patients who tolerate 100 mg of SUBLOCADE monthly, but do not demonstrate a satisfactory clinical response. Maintenance doses should be administered with at least 26 days between injections.

Table 1 Recommended Dosing Schedule
Previous Dose of TM BUP | TM BUP | SUBLOCADE
Previous Dose of TM BUP | Initial Dose | Injection #1 | Injection #2 a | Maintenance Doseb
Initiation in patients not already receiving buprenorphine
NA | 4 mgc | 300 mg | 300 mg | 100 mg
Transition of patients already receiving transmucosal buprenorphine
8 – 24 mg/day | NA | 300 mg | 300 mgd | 100 mg
TM BUP, transmucosal buprenorphine; NA, not applicable
aThe second injection may be administered as early as 1 week and up to 1 month after the initial injection based on patient need.
bA monthly maintenance dosage of 300 mg may be considered in patients who tolerate SUBLOCADE, but do not demonstrate a satisfactory clinical response.
cOn induction day, additional transmucosal buprenorphine may be administered as needed to manage withdrawal symptoms. Monitor patients for 1 hour to confirm tolerability before administering the first injection of SUBLOCADE.
dPatients established on long-term treatment and whose symptoms are controlled with 8 mg to 18 mg daily of transmucosal buprenorphine may receive 100 mg of SUBLOCADE as their second dose if symptoms remain controlled following the initial dose of 300 mg.

Missed doses

A patient who misses a maintenance dose should receive the next dose as soon as possible, with the following dose given at least 26 days later. Occasional delays in dosing up to 2 weeks are not expected to have a clinically significant impact on treatment effect.

For patients in established treatment of 100 mg monthly, there may be instances when allowance for a two-month dosing interval may be appropriate (e.g., extended travel); in those instances, a single 300 mg dose may be given to cover a two-month period. Thereafter, the 100 mg monthly regimen would resume. Patients should be cautioned that the peak plasma level after injection of a 300 mg dose will be higher than their usual monthly dose and that they may experience sedation or other buprenorphine- related effects.

2.4 Clinical Supervision

Periodic assessment is necessary to determine effectiveness of the treatment plan and overall patient progress. When evaluating the patient, examine the injection site for signs of infection or evidence of tampering or attempts to remove the depot.

Due to the chronic nature of opioid use disorder, the need for continuing medication-assisted treatment should be re-evaluated periodically. There is no maximum recommended duration of maintenance treatment. For some patients, treatment may continue indefinitely. If considering stopping treatment, the clinical status of the patient should be considered.

If SUBLOCADE is discontinued, its extended-release characteristics should be considered and the patient should be monitored for several months for signs and symptoms of withdrawal and treated appropriately. After steady-state has been achieved (4-6 months), patients discontinuing SUBLOCADE may have detectable plasma and urine levels of buprenorphine for twelve months or longer [see Clinical Pharmacology (12.3)] .

2.5 Instructions for Use

IMPORTANT INFORMATION:

- For subcutaneous injection only. Do not inject intravenously, intramuscularly, or intradermally [see Warnings and Precautions (5.1, 5.6)] .
- To be prepared and administered by a healthcare provider only.
- Read the instructions carefully before handling the product.
- As a universal precaution, always wear gloves.
- SUBLOCADE must be injected into the subcutaneous tissue of the abdomen, thigh, buttock, or back of the upper arm.
- Remove SUBLOCADE from the refrigerator prior to administration. The product requires at least 15 minutes to reach room temperature. Do not open the foil pouch until the patient has arrived for his or her injection.
- Discard SUBLOCADE if left at room temperature for longer than 12 weeks.
- Do not attach the needle until time of administration.

STEP 1: GETTING READY

Remove the foil pouch and safety needle from the carton. Open the pouch and remove the syringe.

Discard the oxygen absorber pack. It is not needed.

Figure 1

STEP 2: CHECK THE LIQUID CLARITY

Check that the medication does not contain contaminants or particles. SUBLOCADE ranges from colorless to yellow to amber. Variations of color within this range do not affect the potency of the product.

Parenteral drug products should be inspected visually for particulate matter and discoloration prior to administration, whenever solution and container permit.

Figure 2

STEP 3: ATTACH THE SAFETY NEEDLE

Remove the cap from the syringe and the safety needle supplied in the carton from its sterile package.

Gently twist the needle clockwise until it is tight and firmly attached.

Do not remove the plastic cover from the needle.

Figure 3

STEP 4: PREPARE THE INJECTION SITE

Choose one of the following body regions for subcutaneous injection (see Figure 4):

- Abdomen between the transpyloric and transtubercular planes
- Back of the upper arm
- Buttock
- Thigh

Ensure that the selected injection site has adequate subcutaneous tissue that is free of skin conditions (e.g., nodules, lesions, excessive pigment).

Do not inject into an area where the skin is irritated, reddened, bruised, infected or scarred in any way.

To avoid irritation, rotate injection sites.

Clean the injection site well with an alcohol swab.

Figure 4

STEP 5: REMOVE EXCESS AIR FROM SYRINGE

Hold the syringe upright for several seconds to allow air bubbles to rise. Due to the viscous nature of the medication, bubbles will not rise as quickly as those in an aqueous solution.

Remove needle cover and slowly depress the plunger to push out the excess air from the syringe.

- Small bubbles may remain in the medication. Large air gaps, however, can be minimized by pulling back on the plunger rod to pop air bubbles prior to expelling the air very slowly. Air should be expelled very carefully to avoid loss of medication.

If medication is seen at the needle tip, pull back slightly on the plunger to prevent medication spillage.

Figure 5

STEP 6: PINCH THE INJECTION SITE

Pinch the skin around the injection area. Be sure to pinch enough skin to accommodate the size of the needle. Lift the adipose tissue from the underlying muscle to prevent accidental intramuscular injection.

Figure 6

STEP 7: INJECT THE MEDICATION

SUBLOCADE is for subcutaneous injection only.Do not inject intravenously, intramuscularly, or intradermally [see Warnings and Precautions (5.1, 5.6)] .

Insert needle fully into the subcutaneous tissue. Actual angle of injection will depend on the amount of subcutaneous tissue.

Use a slow, steady push to inject the medication. Continue pushing until all of the medication is given.

Figure 7

STEP 8: WITHDRAW THE NEEDLE

Withdraw the needle at the same angle used for insertion and release the pinched skin.

Do not rub the injection area after the injection. There may be a small amount of blood or fluid at the injection site; wipe with a cotton ball or gauze before applying a gauze pad or bandage using minimal pressure.

Figure 8

STEP 9: LOCK THE NEEDLE GUARD AND DISCARD THE SYRINGE

Lock the needle guard into place by pushing it against a hard surface such as a table (Figure 9).

Dispose of all syringe components in a secure sharps disposal container.

Figure 9

STEP 10: INSTRUCT THE PATIENT

Advise the patient that they may have a lump for several weeks that will decrease in size over time. Instruct the patient not to rub or massage the injection site and to be aware of the placement of any restrictive clothing, such as belts, waistbands, or sleeves.

2.6 Limits on Distribution

SUBLOCADE is subject to a risk evaluation and mitigation strategy (REMS) program that includes, among other elements, a restricted distribution system. The purpose of the restricted distribution system is to ensure that SUBLOCADE is only administered by a health care provider [see Warnings and Precautions (5.2)] .

2.7 Removal of the Depot

In the event the depot must be removed, it can be surgically excised under local anesthesia within 14 days of injection. Only the most recently-injected depot can be removed.

The removed depot should be handled with adequate security, accountability, and proper disposal, per facility procedure for a Schedule III drug product and pharmaceutical biohazardous waste, and per applicable federal, state, and local regulations.

The residual plasma concentrations from previous injections will decrease gradually over subsequent months [see Clinical Pharmacology (12.3)] .

Patients who have the depot removed should be monitored for signs and symptoms of withdrawal and treated appropriately [see Warnings and Precautions (5.9)] .

3 DOSAGE FORMS AND STRENGTHS

SUBLOCADE injection is available in dosage strengths of 100 mg/0.5 mL and 300 mg/1.5 mL buprenorphine. Each injection is a sterile, clear, colorless to yellow to amber solution provided in a single-dose, prefilled syringe with a 19 gauge 5/8-inch needle.

4 CONTRAINDICATIONS

SUBLOCADE should not be administered to patients who have been shown to be hypersensitive to buprenorphine or any component of the ATRIGEL®delivery system [see Warnings and Precautions (5.11)] .

5 WARNINGS AND PRECAUTIONS

5.1 Risk of Serious Harm or Death With Intravenous Administration

Intravenous injection presents significant risk of serious harm or death as SUBLOCADE forms a solid mass upon contact with body fluids. Occlusion, local tissue damage, and thrombo-embolic events, including life threatening pulmonary emboli, could result if administered intravenously [see Warnings and Precautions (5.2), Drug Abuse and Dependence (9.2)] . Do not administer intravenously, intramuscularly, or intradermally [see Warnings and Precautions (5.6)] .

5.2 SUBLOCADE Risk Evaluation and Mitigation Strategy (REMS) Program

SUBLOCADE is available only through a restricted program called the SUBLOCADE REMS Program because of the risk of serious harm or death that could result from intravenous self-administration. The goal of the REMS is to mitigate serious harm or death that could result from intravenous self-administration by ensuring that healthcare settings and pharmacies are certified and only dispense SUBLOCADE directly to a healthcare provider for administration by a healthcare provider.

Notable requirements of the SUBLOCADE REMS Program include the following:

- Healthcare Settings and Pharmacies that order and dispense SUBLOCADE must be certified in the SUBLOCADE REMS Program.
- Certified Healthcare Settings and Pharmacies must establish processes and procedures to verify SUBLOCADE is provided directly to a healthcare provider for administration by a healthcare provider, and the drug is not dispensed to the patient.
- Certified Healthcare Settings and Pharmacies must not distribute, transfer, loan, or sell SUBLOCADE.

Further information is available at www.SublocadeREMS.com or call 1-866-258-3905.

5.3 Addiction, Abuse, and Misuse

SUBLOCADE contains buprenorphine, a Schedule III controlled substance that can be abused in a manner similar to other opioids. Buprenorphine is sought by people with opioid use disorder and is subject to criminal diversion. Monitor all patients for progression of opioid use disorder and addictive behaviors [see Drug Abuse and Dependence (9.2)] .

5.4 Risk of Life-Threatening Respiratory and Central Nervous System (CNS) Depression

Buprenorphine has been associated with life-threatening respiratory depression and death. Many, but not all, postmarketing reports regarding coma and death involved misuse by self-injection or were associated with the concomitant use of buprenorphine and benzodiazepines or other CNS depressants, including alcohol. Warn patients of the potential danger of self-administration of benzodiazepines or other CNS depressants while under treatment with SUBLOCADE [see Warnings and Precautions (5.5), Drug Interactions (7), Patient Counseling Information (17)].

Use SUBLOCADE with caution in patients with compromised respiratory function (e.g., chronic obstructive pulmonary disease, cor pulmonale, decreased respiratory reserve, hypoxia, hypercapnia, or pre-existing respiratory depression).

Due to its extended-release characteristics, if SUBLOCADE is discontinued as a result of compromised respiratory function, monitor patients for ongoing buprenorphine effects for several months.

Educate patients and caregivers on how to recognize respiratory depression and emphasize the importance of calling 911 or getting emergency medical help right away in the event of a known or suspected overdose [see Patient Counseling Information (17)] .

Opioids can cause sleep-related breathing disorders including central sleep apnea (CSA) and sleep-related hypoxemia. Opioid use increases the risk of CSA in a dose-dependent fashion. In patients who present with CSA, consider decreasing the opioid dosage using best practices for opioid taper [see Dosage and Administration (2.7)] .

Patient Access to an Opioid Overdose Reversal Agent for the Emergency Treatment of Opioid Overdose

Inform patients and caregivers about opioid overdose reversal agents (e.g., naloxone, nalmefene) and discuss the importance of having access to an opioid overdose reversal agent. Because patients being treated for opioid use disorder have the potential for relapse, putting them at risk for opioid overdose, strongly consider recommending or prescribing an opioid overdose reversal agent for the emergency treatment of an opioid overdose, both when initiating and renewing treatment with SUBLOCADE. Also consider recommending or prescribing such an agent if the patient has household members (including children) or other close contacts at risk for accidental ingestion or opioid overdose [see Dosage and Administration (2.2)].

Discuss the options for obtaining an opioid overdose reversal agent (e.g., prescription, over-the-counter, or as part of a community-based program).

There are important differences among the opioid overdose reversal agents, such as route of administration, product strength, approved patient age range, and pharmacokinetics. Be familiar with these differences, as outlined in the approved labeling for those products, prior to recommending or prescribing such an agent.

Advise patients and caregivers that an opioid overdose reversal agent, such as naloxone or nalmefene, may also be administered for a known or suspected overdose with buprenorphine itself. Higher than normal doses and repeated administration of an opioid overdose reversal agent may be necessary due to the long duration of action of buprenorphine and its affinity for the mu-opioid receptor [see Overdosage (10)] .

Educate patients and caregivers on how to recognize respiratory depression, and how to use an opioid overdose reversal agent for the emergency treatment of opioid overdose. Emphasize the importance of calling 911 or getting emergency medical help, even if an opioid overdose reversal agent is administered.

5.5 Managing Risks From Concomitant Use of Benzodiazepines or Other CNS Depressants With Buprenorphine

Concomitant use of buprenorphine and benzodiazepines and/or other CNS depressants (e.g., alcohol, non-benzodiazepine sedative/hypnotics, anxiolytics, tranquilizers, muscle relaxants, general anesthetics, antipsychotics, gabapentinoids [gabapentin or pregabalin], and other opioids) increases the risk of adverse reactions including overdose, respiratory depression, and death. Medication-assisted treatment of opioid use disorder, however, should not be categorically denied to patients taking these drugs. Prohibiting or creating barriers to treatment can pose an even greater risk of morbidity and mortality due to the opioid use disorder alone.

As a routine part of orientation to buprenorphine treatment, educate patients about the risks of concomitant use of benzodiazepines, sedatives, opioid analgesics, and alcohol.

Develop strategies to manage use of prescribed or illicit benzodiazepines or other CNS depressants at initiation of buprenorphine treatment, or if it emerges as a concern during treatment. Adjustments to induction procedures and additional monitoring may be required. There is no evidence to support dose limitations or arbitrary caps of buprenorphine as a strategy to address benzodiazepine use in buprenorphine-treated patients. However, if a patient is sedated at the time of buprenorphine dosing, delay or omit the buprenorphine dose if appropriate.

Cessation of benzodiazepines or other CNS depressants is preferred in most cases of concomitant use with buprenorphine. In some cases, monitoring in a higher level of care for taper may be appropriate. In others, gradually tapering a patient off of a prescribed benzodiazepine or other CNS depressant or decreasing to the lowest effective dose may be appropriate.

For patients in buprenorphine treatment, benzodiazepines are not the treatment of choice for anxiety or insomnia. Before co-prescribing benzodiazepines, ensure that patients are appropriately diagnosed and consider alternative medications and non-pharmacologic treatments to address anxiety or insomnia. Ensure that other healthcare providers prescribing benzodiazepines or other CNS depressants are aware of the patient's buprenorphine treatment and coordinate care to minimize the risks associated with concomitant use.

If concomitant use is warranted, strongly consider recommending or prescribing an opioid overdose reversal agent, as is recommended for all patients on buprenorphine treatment for opioid use disorder [see Warnings and Precautions (5.4)].

In addition, take measures to confirm that patients are taking their medications as prescribed and are not diverting or supplementing with illicit drugs. Toxicology screening should test for prescribed and illicit benzodiazepines [see Drug Interactions (7)] .

5.6 Risk of Serious Injection Site Reactions

Injection site reactions are most commonly manifested by pain, erythema and pruritus. In some post-marketing case reports injection site reactions have involved abscess, ulceration, and necrosis. Some cases resulted in surgical depot removal, debridement, antibiotic administration, and SUBLOCADE discontinuation. The likelihood of serious injection site reactions may be increased with inadvertent intramuscular or intradermal administration. Carefully review injection technique [see Instructions for Use (2.5)] . Evaluate and treat serious injection site reactions as appropriate.

5.7 Neonatal Opioid Withdrawal Syndrome

Neonatal opioid withdrawal syndrome (NOWS) is an expected and treatable outcome of prolonged use of opioids during pregnancy, whether that use is medically-authorized or illicit. Unlike opioid withdrawal syndrome in adults, NOWS may be life-threatening if not recognized and treated in the neonate. Healthcare professionals should observe newborns for signs of NOWS and manage accordingly [see Use in Specific Populations (8.1)] .

Advise pregnant women receiving opioid addiction treatment with SUBLOCADE of the risk of neonatal opioid withdrawal syndrome and ensure that appropriate treatment will be available [see Use in Specific Populations (8.1)] . This risk should be balanced against the risk of untreated opioid addiction which often results in continued or relapsing illicit opioid use and is associated with poor pregnancy outcomes. Therefore, prescribers should discuss the importance of management of opioid addiction throughout pregnancy.

5.8 Adrenal Insufficiency

Cases of adrenal insufficiency have been reported with opioid use, more often following greater than one month of use. Presentation of adrenal insufficiency may include non-specific symptoms and signs including nausea, vomiting, anorexia, fatigue, weakness, dizziness, and low blood pressure. If adrenal insufficiency is suspected, confirm the diagnosis with diagnostic testing as soon as possible. If adrenal insufficiency is diagnosed, treat with physiologic replacement doses of corticosteroids. Wean the patient off the opioid to allow adrenal function to recover and continue corticosteroid treatment until adrenal function recovers. Other opioids may be tried as some cases reported use of a different opioid without recurrence of adrenal insufficiency. The information available does not identify any particular opioids as being more likely to be associated with adrenal insufficiency.

5.9 Risk of Opioid Withdrawal With Abrupt Discontinuation of SUBLOCADE Treatment

Buprenorphine is a partial agonist at the mu-opioid receptor and chronic administration produces physical dependence of the opioid type, characterized by withdrawal signs and symptoms upon abrupt discontinuation. The withdrawal syndrome is milder than that seen with full agonists and may be delayed in onset [see Drug Abuse and Dependence (9.3)] .

Withdrawal signs and symptoms were not observed in the month following discontinuation of SUBLOCADE. Considering the long half-life, any withdrawal signs and symptoms that may occur would be expected to be delayed [see Clinical Pharmacology (12.2)] . Model simulations indicate that steady-state buprenorphine plasma concentrations decreased slowly over time following the last injection and remained at therapeutic levels for 2 to 5 months on average, depending on the dosage administered (100 or 300 mg, respectively).

Patients who elect to discontinue treatment with SUBLOCADE should be monitored for withdrawal signs and symptoms. Consider transmucosal buprenorphine if needed to treat withdrawal after discontinuing SUBLOCADE.

5.10 Risk of Hepatitis, Hepatic Events

Cases of cytolytic hepatitis and hepatitis with jaundice have been observed in individuals receiving buprenorphine in clinical trials and through postmarketing adverse event reports. The spectrum of abnormalities ranges from transient asymptomatic elevations in hepatic transaminases to case reports of death, hepatic failure, hepatic necrosis, hepatorenal syndrome, and hepatic encephalopathy. In many cases, the presence of pre-existing liver enzyme abnormalities, infection with hepatitis B or hepatitis C virus, concomitant usage of other potentially hepatotoxic drugs, and ongoing injecting drug use may have played a causative or contributory role. In other cases, insufficient data were available to determine the etiology of the abnormality. Withdrawal of buprenorphine has resulted in amelioration of acute hepatitis in some cases, however, in other cases no dose reduction was necessary. The possibility exists that buprenorphine had a causative or contributory role in the development of the hepatic abnormality in some cases. In one subject in the SUBLOCADE clinical program, surgical removal was followed by improvement in liver enzymes.

Liver function tests, prior to initiation of treatment, are recommended to establish a baseline. Monthly monitoring of liver function during treatment, particularly with 300 mg maintenance dose, is also recommended. An etiological evaluation is recommended when a hepatic adverse event is suspected.

5.11 Hypersensitivity Reactions

Cases of hypersensitivity to buprenorphine-containing products have been reported both in clinical trials and in the postmarketing experience. Cases of bronchospasm, angioneurotic edema, and anaphylactic shock have been reported. The most common signs and symptoms include rashes, hives, and pruritus. A history of hypersensitivity to buprenorphine is a contraindication to the use of SUBLOCADE [see Contraindications (4)] .

5.12 Precipitation of Opioid Withdrawal in Patients Dependent on Full Agonist Opioids

Because of the partial opioid agonist properties of buprenorphine, buprenorphine may precipitate opioid withdrawal signs and symptoms in persons who are currently physically dependent on full opioid agonists if administered before the effects of the full opioid agonist have subsided, at least 6 hours for short-acting opioids (e.g., heroin, morphine) and 24 hours for long-acting opioids (e.g., methadone). Verify that patients have tolerated transmucosal buprenorphine before administering the first injection of SUBLOCADE.

5.13 Risks Associated With Treatment of Emergent Acute Pain

While on SUBLOCADE, situations may arise where patients need acute pain management, or may require anesthesia. Treat patients receiving SUBLOCADE with a non-opioid analgesic whenever possible. Patients requiring opioid therapy for analgesia may be treated with a high-affinity full opioid analgesic under the supervision of a physician, with particular attention to respiratory function. Higher doses may be required for analgesic effect. Therefore, a higher potential for toxicity exists with opioid administration. If opioid therapy is required as part of anesthesia, patients should be continuously monitored in an anesthesia care setting by persons not involved in the conduct of the surgical or diagnostic procedure. The opioid therapy should be provided by individuals specifically trained in the use of anesthetic drugs and the management of the respiratory effects of potent opioids, specifically the establishment and maintenance of a patent airway and assisted ventilation.

Advise patients of the importance of instructing their family members, in the event of emergency, to inform the treating healthcare provider or emergency room staff that the patient is physically dependent on an opioid and that the patient is being treated with SUBLOCADE [see Patient Counseling Information (17)] .

The above guidance should also be considered for any patient who has been treated with SUBLOCADE within the last 6 months.

5.14 Use in Opioid Naïve Patients

There have been reported deaths of opioid naïve individuals who received a 2 mg dose of buprenorphine as a sublingual tablet. SUBLOCADE is not appropriate for use in opioid naïve patients.

5.15 Use in Patients With Impaired Hepatic Function

In a pharmacokinetic study with transmucosal buprenorphine, buprenorphine plasma levels were found to be higher and the half-life was found to be longer in subjects with moderate and severe hepatic impairment, but not in subjects with mild hepatic impairment. The effect of hepatic impairment on the pharmacokinetics of SUBLOCADE has not been studied.

Because of the long-acting nature of the product, adjustments to dosages of SUBLOCADE are not rapidly reflected in plasma buprenorphine levels. Because buprenorphine levels cannot be rapidly decreased, patients with pre-existing moderate to severe hepatic impairment are not candidates for treatment with SUBLOCADE.

Patients who develop moderate to severe hepatic impairment while being treated with SUBLOCADE should be monitored for several months for signs and symptoms of toxicity or overdose caused by increased levels of buprenorphine [see Use in Specific Populations (8.6), Clinical Pharmacology (12.3)] .

5.16 QTc Prolongation

Thorough QT studies with buprenorphine products have demonstrated QT prolongation ≤ 15 msec. This QTc prolongation effect does not appear to be mediated by hERG channels. Based on these two findings, buprenorphine is unlikely to be pro-arrhythmic when used alone in patients without risk factors. The risk of combining buprenorphine with other QT-prolonging agents is not known.

Consider these observations in clinical decisions when prescribing SUBLOCADE to patients with risk factors such as hypokalemia, bradycardia, recent conversion from atrial fibrillation, congestive heart failure, digitalis therapy, baseline QT prolongation, subclinical long-QT syndrome, or severe hypomagnesemia.

5.17 Impairment of Ability to Drive or Operate Machinery

SUBLOCADE may impair the mental or physical abilities required for the performance of potentially dangerous tasks such as driving a car or operating machinery especially during the first few days following treatment and dose adjustment. Buprenorphine plasma levels accumulate during the first two months and are maintained with the 100 mg maintenance dose; further accumulation occurs with the 300 mg maintenance dose, which achieves steady-state after the fourth monthly injection. Caution patients about driving or operating hazardous machinery until they are reasonably certain that SUBLOCADE does not adversely affect their ability to engage in such activities.

5.18 Orthostatic Hypotension

Buprenorphine may produce orthostatic hypotension in ambulatory patients.

5.19 Elevation of Cerebrospinal Fluid Pressure

Buprenorphine may elevate cerebrospinal fluid pressure and should be used with caution in patients with head injury, intracranial lesions, and other circumstances when cerebrospinal pressure may be increased. Buprenorphine can produce miosis and changes in the level of consciousness that may interfere with patient evaluation.

5.20 Elevation of Intracholedochal Pressure

Buprenorphine has been shown to increase intracholedochal pressure, as do other opioids, and thus should be administered with caution to patients with dysfunction of the biliary tract.

5.21 Effects in Acute Abdominal Conditions

Buprenorphine may obscure the diagnosis or clinical course of patients with acute abdominal conditions.

5.22 Unintentional Pediatric Exposure

Buprenorphine can cause severe, possibly fatal, respiratory depression in children who are accidentally exposed to it.

6 ADVERSE REACTIONS

The following adverse reactions are discussed in more detail in other sections of the labeling:

- Addiction, Abuse, and Misuse [see Warnings and Precautions (5.3)]
- Respiratory and CNS Depression [see Warnings and Precautions (5.4)]
- Neonatal Opioid Withdrawal Syndrome [see Warnings and Precautions (5.7)]
- Adrenal Insufficiency [see Warnings and Precautions (5.8)]
- Opioid Withdrawal [see Warnings and Precautions (5.9, 5.12)]
- Hepatitis, Hepatic Events [see Warnings and Precautions (5.10)]
- Hypersensitivity Reactions [see Warnings and Precautions (5.11)]
- Orthostatic Hypotension [see Warnings and Precautions (5.18)]
- Elevation of Cerebrospinal Fluid Pressure [see Warnings and Precautions (5.19)]
- Elevation of Intracholedochal Pressure [see Warnings and Precautions (5.20)]

6.1 Clinical Trials Experience

Because clinical trials are conducted under widely varying conditions, adverse reaction rates observed in the clinical trials of a drug cannot be directly compared to rates in the clinical trials of another drug and may not reflect the rates observed in practice.

The safety of SUBLOCADE was evaluated in 848 opioid-dependent subjects (see Table 2). In these studies, there was a total of 557 subjects who received at least 6 monthly SC injections of SUBLOCADE and 138 subjects who received 12 monthly SC injections. Adverse events led to premature discontinuation in 4% of the group receiving SUBLOCADE compared with 2% in the placebo group (13-0001, NCT02357901).

In the Phase 3 open-label study (13-0003, NCT02510014), adverse events leading to drug dose reductions were reported in 7.3% of subjects receiving SUBLOCADE.

Table 2 Total Subjects Exposed to SUBLOCADE
Study 13-0001 (NCT02357901) Up to 6 Injections |  |  | Study 13-0003 (NCT02510014) |  |  |  | Total Subjects Exposed To SUBLOCADE
Study 13-0001 (NCT02357901) Up to 6 Injections |  |  | Roll-Over Up to 6 Injections |  |  | De-Novo Up to 12 Injections | Total Subjects Exposed To SUBLOCADE
SUBLOCADE 300/100 mg | SUBLOCADE 300/300 mg | Placebo | From SUBLOCADE 300/100 mg To SUBLOCADE 300/Flex† | From SUBLOCADE 300/300 mg To SUBLOCADE 300/Flex† | From Placebo To SUBLOCADE 300/Flex† | SUBLOCADE 300/Flex | Total Subjects Exposed To SUBLOCADE
N = 203 | N = 201 | N = 100* | N = 112‡ | N = 113‡ | N = 32 | N = 412 | N = 848
*Not included in total subjects exposed to SUBLOCADE
† FLEX = 300 mg initial dose with an option to receive either 100 mg or 300 mg for subsequent dosing per clinician's discretion
‡ = Not included in total unique subjects exposed to SUBLOCADE, already accounted for in Study 13-0001 section of table

Table 3shows the non-injection site-related adverse reactions (ADRs) for the groups receiving SUBLOCADE 300/300 mg (6 doses of 300 mg SC injections) 300/100 mg (300 mg SC injections for the first two doses followed by 4 doses of 100 mg SC injections) and placebo (volume-matched ATRIGEL®delivery system subcutaneous injections) reported following administration in the 6 month, double-blind, placebo-controlled study. The systemic safety profile for SUBLOCADE, given by a healthcare provider in clinical trials, was consistent with the known safety profile of transmucosal buprenorphine. Common adverse reactions associated with buprenorphine included constipation, nausea, vomiting, abnormal liver enzymes, headache, sedation and somnolence. Dose dependent hepatic effects observed in the Phase 3, double-blind study (13-0001, NCT02357901) included the incidence of ALT more than 3 times the upper limit of normal (> 3 × ULN) in 12.4%, 5.4%, and 4.0% of the SUBLOCADE 300/300-mg, SUBLOCADE 300/100-mg, and placebo groups, respectively. The incidence of AST > 3 × ULN was 11.4%, 7.9%, and 1.0%, respectively. Adverse drug reactions [by MedDRA Preferred Terms (PT)] reported in at least 2% of subjects receiving SUBLOCADE are grouped by System Organ Class (SOC).

Table 3 Adverse Reactions for Phase 3 Double-Blind Study: ≥ 2% of Subjects Receiving SUBLOCADE
System Organ Class Preferred Term | PLACEBO | SUBLOCADE 300/100 mg | SUBLOCADE 300/300 mg
 | Count (%) | Count (%) | Count (%)
Total | N = 100 | N = 203 | N = 201
Gastrointestinal disorders | 12 (12%) | 51 (25.1%) | 45 (22.4%)
Constipation | 0 | 19 (9.4) | 16 (8)
Nausea | 5 (5) | 18 (8.9) | 16 (8)
Vomiting | 4 (4) | 19 (9.4) | 11 (5.5)
General disorders and administration site conditions | 17 (17%) | 40 (19.7%) | 49 (24.4%)
Fatigue | 3 (3) | 8 (3.9) | 12 (6)
Investigations* | 2 (2%) | 21 (10.3%) | 19 (9.5%)
Alanine aminotransferase increased (ALT) | 0 | 2 (1) | 10 (5)
Aspartate aminotransferase increased (AST) | 0 | 7 (3.4) | 9 (4.5)
Blood creatine phosphokinase increased (CPK) | 1 (1) | 11 (5.4) | 5 (2.5)
Gamma-glutamyl transferase increased (GGT) | 1 (1) | 6 (3) | 8 (4)
Nervous system disorders | 7 (7%) | 35 (17.2%) | 25 (12.4%)
Headache | 6 (6) | 19 (9.4) | 17 (8.5)
Sedation | 0 | 7 (3.4) | 3 (1.5)
Dizziness | 2 (2) | 5 (2.5) | 3 (1.5)
Somnolence | 0 | 10 (4.9) | 4 (2)
*There were no cases of serious liver injury attributed to study drug.

Table 4shows the injection site-related adverse events reported by ≥ 2 subjects in the Phase 3 studies. Most injection site adverse drug reactions (ADRs) were of mild to moderate severity, with one report of severe injection site pruritus. None of the injection site reactions were serious. One reaction, an injection site ulcer, led to study treatment discontinuation.

Table 4 Injection Site Adverse Drug Reactions Reported by ≥ 2 Subjects in the Phase 3 Studies
Preferred term, n (%) | 13-0001 (Ph3DB) |  |  | 13-0003 (Ph3OL) |  |  |  | All Phase 3*
Preferred term, n (%) | 13-0001 (Ph3DB) |  |  | Roll–over |  |  | De-novo | All Phase 3*
Preferred term, n (%) | SUBLOCADE 300/300 (N = 201) | SUBLOCADE 300/100 (N = 203) | Placebo (N = 100) | SUBLOCADE 300 → SUBLOCADE 300/Flex (N = 113) | SUBLOCADE 100 → SUBLOCADE 300/Flex (N = 112) | Placebo → SUBLOCADE 300/Flex (N = 32) | SUBLOCADE 300/Flex (N = 412) | Total SUBLOCADE (N = 848)
Subjects with any injection site reactions | 38 (18.9%) | 28 (13.8%) | 9 (9.0%) | 6 (5.3%) | 13 (11.6%) | 2 (6.3%) | 61 (14.8%) | 140 (16.5%)
Injection site pain | 12 (6.0%) | 10 (4.9%) | 3 (3.0%) | 4 (3.5%) | 2 (1.8%) | 2 (6.3%) | 33 (8.0%) | 61 (7.2%)
Injection site pruritus | 19 (9.5%) | 13 (6.4%) | 4 (4.0%) | 2 (1.8%) | 6 (5.4%) | 1 (3.1%) | 17 (4.1%) | 56 (6.6%)
Injection site erythema | 6 (3.0%) | 9 (4.4%) | 0 | 1 (0.9%) | 4 (3.6%) | 0 | 21 (5.1%) | 40 (4.7%)
Injection site induration | 2 (1.0%) | 2 (1.0%) | 0 | 0 | 1 (0.9%) | 0 | 7 (1.7%) | 12 (1.4%)
Injection site bruising | 2 (1.0%) | 2 (1.0%) | 0 | 0 | 0 | 0 | 2 (0.5%) | 6 (0.7%)
Injection site swelling | 1 (0.5%) | 2 (1.0%) | 0 | 1 (0.9%) | 1 (0.9%) | 0 | 1 (0.2%) | 6 (0.7%)
Injection site discomfort | 1 (0.5%) | 1 (0.5%) | 0 | 0 | 0 | 0 | 3 (0.7%) | 5 (0.6%)
Injection site reaction | 1 (0.5%) | 0 | 0 | 0 | 3 (2.7%) | 0 | 1 (0.2%) | 5 (0.6%)
Injection site cellulitis | 0 | 1 (0.5%) | 0 | 0 | 0 | 0 | 2 (0.5%) | 3 (0.4%)
Injection site infection | 1 (0.5%) | 0 | 1 (1.0%) | 0 | 0 | 0 | 2 (0.5%) | 3 (0.4%)
*Patients received SUBOXONE film for a run-in period before they switched to SUBLOCADE injection.

Longer-term experience

In an interim analysis of the ongoing open-label long-term safety study (13-0003), safety was evaluated for up to 12 injections over the course of a year (see Table 2). Adverse events were reported for 432 of 669 subjects during the treatment period. The overall adverse event profile was similar to the double-blind trial described above.

Rapid Induction study

The proportion of patients who experienced an adverse event associated with opioid withdrawal was 31.4% in patients who received SUBLOCADE injection after an initial dose of transmucosal buprenorphine (rapid induction) and 25.1% in those who first received transmucosal buprenorphine for at least 7 days (standard induction). Three fentanyl positive patients in the rapid induction arm had serious adverse events associated with opioid withdrawal, and none in the standard induction arm.

6.2 Postmarketing Experience

The most frequently reported systemic postmarketing adverse event observed with buprenorphine sublingual tablets was drug misuse or abuse. The most frequently reported systemic postmarketing adverse event with buprenorphine/naloxone sublingual tablets and film was peripheral edema.

The following adverse reactions have been identified during post-approval use of buprenorphine. Because these reactions are reported voluntarily from a population of uncertain size, it is not always possible to reliably estimate their frequency or establish a causal relationship to drug exposure.

Serotonin syndrome:Cases of serotonin syndrome, a potentially life-threatening condition, have been reported during concomitant use of opioids with serotonergic drugs.

Adrenal insufficiency:Cases of adrenal insufficiency have been reported with opioid use, more often following greater than one month of use.

Anaphylaxis:Anaphylaxis has been reported with ingredients contained in SUBLOCADE.

Androgen deficiency:Cases of androgen deficiency have occurred with chronic use of opioids [see Clinical Pharmacology (12.2)] .

Hypoglycemia:Cases of hypoglycemia have been reported in patients taking opioids. Most reports were in patients with at least one predisposing risk factor (e.g., diabetes).

Opioid-induced esophageal dysfunction (OIED): Cases of OIED have been reported in patients taking opioids and may occur more frequently in patients taking higher doses of opioids, and/or in patients taking opioids longer term.

7 DRUG INTERACTIONS

Table 5includes clinically significant drug interactions with SUBLOCADE.

Table 5 Clinically Significant Drug Interactions
Benzodiazepines and Other Central Nervous System (CNS) Depressants
Clinical Impact: | Due to additive pharmacologic effects, the concomitant use of benzodiazepines or other CNS depressants, including alcohol, increases the risk of respiratory depression, profound sedation, coma, and death.
Intervention: | Cessation of benzodiazepines or other CNS depressants is preferred in most cases of concomitant use. In some cases, monitoring in a higher level of care for taper may be appropriate. In others, gradually tapering a patient off of a prescribed benzodiazepine or other CNS depressant or decreasing to the lowest effective dose may be appropriate. Similarly, cessation of other CNS depressants is preferred when possible. Before co-prescribing benzodiazepines for anxiety or insomnia, ensure that patients are appropriately diagnosed and consider alternative medications and non-pharmacologic treatments [see Warnings and Precautions (5.4, 5.5)] . If concomitant use is warranted, strongly consider recommending or prescribing an opioid overdose reversal agent, as is recommended for all patients on buprenorphine treatment for opioid use disorder [see Warnings and Precautions (5.4)].
Examples: | Alcohol, benzodiazepines and other sedatives/hypnotics, anxiolytics, tranquilizers, muscle relaxants, general anesthetics, antipsychotics, gabapentinoids (gabapentin or pregabalin), and other opioids.
Inhibitors of CYP3A4
Clinical Impact: | The effects of co-administered CYP3A4 inhibitors on buprenorphine exposure in subjects treated with SUBLOCADE have not been studied and the effects may be dependent on the route of administration; however, such interactions have been established in studies using transmucosal buprenorphine. Buprenorphine is metabolized to norbuprenorphine primarily by CYP3A4; therefore, potential interactions may occur when SUBLOCADE is given concurrently with agents that affect CYP3A4 activity. The concomitant use of sublingual buprenorphine and CYP3A4 inhibitors (e.g., ketoconazole) can increase the plasma concentration of buprenorphine, resulting in increased or prolonged opioid effects.
Intervention: | Patients who transfer to SUBLOCADE treatment from a regimen of transmucosal buprenorphine used concomitantly with CYP3A4 inhibitors [e.g., azole antifungals such as ketoconazole, macrolide antibiotics such as erythromycin, and HIV protease inhibitors (e.g., ritonavir, indinavir, and saquinavir)] should be monitored to ensure that the plasma buprenorphine level provided by SUBLOCADE is adequate. If patients already on SUBLOCADE require newly-initiated treatment with CYP3A4 inhibitors, the patients should be monitored for signs and symptoms of over-medication. Within 2 weeks of SUBLOCADE administration, if signs and symptoms of buprenorphine toxicity or overdose occur but the concomitant medication cannot be reduced or discontinued, it may be necessary to remove the depot and treat the patient with a formulation of buprenorphine that permits dose adjustments. Conversely, if a patient has been stabilized on SUBLOCADE in the setting of concomitant medication that is a CYP3A4 inhibitor, and the concomitant medication is discontinued, the patient should be monitored for withdrawal. If the dose of SUBLOCADE is not adequate in the absence of the concomitant medication, that patient should be transitioned back to a formulation of buprenorphine that permits dose adjustments.
Examples: | Macrolide antibiotics (e.g., erythromycin), azole-antifungal agents (e.g., ketoconazole), protease inhibitors (e.g., ritonavir)
CYP3A4 Inducers
Clinical Impact: | The effects of co-administered CYP3A4 inducers on buprenorphine exposure in subjects treated with SUBLOCADE have not been studied. Buprenorphine is metabolized to norbuprenorphine primarily by CYP3A4; therefore, potential interactions may occur when SUBLOCADE is given concurrently with agents that affect CYP3A4 activity. CYP3A4 inducers may induce the metabolism of buprenorphine and, therefore, may cause increased clearance of the drug which could lead to a decrease in buprenorphine plasma concentrations, lack of efficacy or, possibly, development of an abstinence syndrome.
Intervention: | Patients who transfer to SUBLOCADE treatment from a regimen of transmucosal buprenorphine used concomitantly with CYP3A4 inducers should be monitored to ensure that the plasma buprenorphine level provided by SUBLOCADE is adequate. If patients already on SUBLOCADE require newly-initiated treatment with CYP3A4 inducers, the patients should be monitored for withdrawal. If the dose of SUBLOCADE is not adequate in the absence of the concomitant medication, and the concomitant medication cannot be reduced or discontinued, that patient should be transitioned back to a formulation of buprenorphine that permits dose adjustments. Conversely, if a patient has been stabilized on SUBLOCADE in the setting of concomitant medication that is a CYP3A4 inducer, and the concomitant medication is discontinued, the patient should be monitored for signs and symptoms of over-medication. Within 2 weeks of SUBLOCADE administration, if the dose provided by SUBLOCADE is excessive in the absence of the concomitant inducer, it may be necessary to remove the SUBLOCADE and treat the patient with a formulation of buprenorphine that permits dose adjustments [see Clinical Pharmacology (12.3)] .
Examples: | Rifampin, carbamazepine, phenytoin, phenobarbital
Antiretrovirals: Non-nucleoside reverse transcriptase inhibitors (NNRTIs)
Clinical Impact: | Non-nucleoside reverse transcriptase inhibitors (NNRTIs) are metabolized principally by CYP3A4. Efavirenz, nevirapine, and etravirine are known CYP3A inducers, whereas delavirdine is a CYP3A inhibitor. Significant pharmacokinetic interactions between NNRTIs (e.g., efavirenz and delavirdine) and sublingual buprenorphine have been shown in clinical studies, but these pharmacokinetic interactions did not result in any significant pharmacodynamic effects.
Intervention: | Patients who are on chronic treatment with SUBLOCADE should be monitored for increase or decrease in therapeutic effects if NNRTIs are added to their treatment regimen.
Examples: | Efavirenz, nevirapine, etravirine, delavirdine
Antiretrovirals: Protease inhibitors (PIs)
Clinical Impact: | Studies have shown some antiretroviral protease inhibitors (PIs) with CYP3A4 inhibitory activity (nelfinavir, lopinavir/ritonavir, ritonavir) have little effect on sublingual buprenorphine pharmacokinetic and no significant pharmacodynamic effects. Other PIs with CYP3A4 inhibitory activity (atazanavir and atazanavir/ritonavir) resulted in elevated levels of buprenorphine and norbuprenorphine after sublingual administration, and patients in one study reported increased sedation. Symptoms of opioid excess have been found in postmarketing reports of patients receiving sublingual buprenorphine and atazanavir with and without ritonavir concomitantly.
Intervention: | If treatment with atazanavir with and without ritonavir must be initiated in a patient already treated with SUBLOCADE, the patient should be monitored for signs and symptoms of over-medication. It may be necessary to remove the depot and treat the patient with a sublingual buprenorphine product that permits rapid dose adjustments.
Examples: | Atazanavir, ritonavir
Antiretrovirals: Nucleoside reverse transcriptase inhibitors (NRTIs)
Clinical Impact: | Nucleoside reverse transcriptase inhibitors (NRTIs) do not appear to induce or inhibit the P450 enzyme pathway, thus no interactions with buprenorphine are expected.
Intervention: | None
Serotonergic Drugs
Clinical Impact: | The concomitant use of opioids with other drugs that affect the serotonergic neurotransmitter system has resulted in serotonin syndrome.
Intervention: | If concomitant use is warranted, carefully monitor the patient for signs and symptoms of serotonin syndrome, particularly during treatment initiation, and during dose adjustment of the serotonergic drug.
Examples: | Selective serotonin reuptake inhibitors (SSRIs), serotonin and norepinephrine reuptake inhibitors (SNRIs), tricyclic antidepressants (TCAs), triptans, 5-HT3 receptor antagonists, drugs that affect the serotonin neurotransmitter system (e.g., mirtazapine, trazodone, tramadol), certain muscle relaxants (i.e., cyclobenzaprine, metaxalone), monoamine oxidase (MAO) inhibitors (those intended to treat psychiatric disorders and also others, such as linezolid and intravenous methylene blue).
Monoamine Oxidase Inhibitors (MAOIs)
Clinical Impact: | MAOI interactions with opioids may manifest as serotonin syndrome or opioid toxicity (e.g., respiratory depression, coma).
Intervention: | The use of SUBLOCADE is not recommended for patients taking MAOIs or within 14 days of stopping such treatment.
Examples: | Phenelzine, tranylcypromine, linezolid
Muscle Relaxants
Clinical Impact: | Buprenorphine may enhance the neuromuscular blocking action of skeletal muscle relaxants and produce an increased degree of respiratory depression.
Intervention: | Monitor patients receiving muscle relaxants and SUBLOCADE for signs of respiratory depression that may be greater than otherwise expected and decrease the dosage of the muscle relaxant as necessary. Due to the risk of respiratory depression with concomitant use of skeletal muscle relaxants and opioids, strongly consider recommending or prescribing an opioid overdose reversal agent, as is recommended for all patients on buprenorphine treatment for opioid use disorder [see Dosage and Administration (2.2), Warnings and Precautions (5.4, 5.5)] .
Examples: | cyclobenzaprine, metaxolone
Diuretics
Clinical Impact: | Opioids can reduce the efficacy of diuretics by inducing the release of antidiuretic hormone.
Intervention: | Monitor patients for signs of diminished diuresis and/or effects on blood pressure and increase the dosage of the diuretic as needed.
Anticholinergic Drugs
Clinical Impact: | The concomitant use of anticholinergic drugs may increase the risk of urinary retention and/or severe constipation, which may lead to paralytic ileus.
Intervention: | Monitor patients for signs of urinary retention or reduced gastric motility when SUBLOCADE is used concomitantly with anticholinergic drugs.

8 USE IN SPECIFIC POPULATIONS

8.1 Pregnancy

Risk Summary

The data on use of buprenorphine, the active ingredient in SUBLOCADE, in pregnancy, are limited; however, these data do not indicate an increased risk of major malformations specifically due to buprenorphine exposure. There are limited data from randomized clinical trials in women maintained on buprenorphine that were not designed appropriately to assess the risk of major malformations [see Human Data] .

Observational studies have reported congenital malformations among buprenorphine‐exposed pregnancies, but were also not designed appropriately to assess the risk of congenital malformations specifically due to buprenorphine exposure [see Human Data] .

In animal reproduction studies with SUBLOCADE, SUBLOCADE administered subcutaneously to pregnant rats and rabbits during the period of organogenesis at a buprenorphine dose equivalent to 38 and 15 times, respectively, the maximum recommended human dose (MRHD) of 300 mg caused embryolethality, which appeared to be attributable primarily to the SUBLOCADE vehicle (ATRIGEL®delivery system). In addition, reduced fetal body weights, increased visceral malformations and skeletal malformations were observed in rats and rabbits at buprenorphine doses equivalent to 38 and 15 times, respectively, the MRHD. These effects were also observed with the ATRIGEL®delivery system alone, but the skeletal and visceral malformations in rat appear at least partially attributable to buprenorphine [see Animal Data] . Based on animal data, advise pregnant women of the potential risk to a fetus.

The estimated background risk of major birth defects and miscarriage for the indicated population is unknown. All pregnancies have a background risk of birth defect, loss, or other adverse outcomes. In the U.S. general population, the estimated background risk of major birth defects and miscarriage in clinically recognized pregnancies is 2 to 4% and 15 to 20%, respectively.

SUBLOCADE should be used during pregnancy only if the potential benefit justifies the potential risk to the fetus.

Clinical Considerations

Disease-associated maternal and embryo-fetal risk

Untreated opioid addiction in pregnancy is associated with adverse obstetrical outcomes such as low birth weight, preterm birth, and fetal death. In addition, untreated opioid addiction often results in continued or relapsing illicit opioid use.

Fetal/neonatal adverse reactions

Neonatal opioid withdrawal syndrome may occur in newborn infants of mothers who are receiving treatment with SUBLOCADE.

Neonatal opioid withdrawal syndrome presents as irritability, hyperactivity and abnormal sleep pattern, high pitched cry, tremor, vomiting, diarrhea, and/or failure to gain weight. Signs of neonatal withdrawal usually occur in the first days after birth. The duration and severity of neonatal opioid withdrawal syndrome may vary. Observe newborns for signs of neonatal opioid withdrawal syndrome and manage accordingly [see Warnings and Precautions (5.7)] .

Labor or Delivery

Opioid-dependent women on buprenorphine maintenance therapy may require additional analgesia during labor. As with all opioids, use of buprenorphine prior to delivery may result in respiratory depression in the newborn. Closely monitor neonates for signs of respiratory depression. An opioid overdose reversal agent, such as naloxone or nalmefene, should be available for reversal of opioid induced respiratory depression in the neonate.

Data

Human Data

Studies have been conducted to evaluate neonatal outcomes in women exposed to buprenorphine during pregnancy. Limited data on malformations from trials, observational studies, case series, and case reports on buprenorphine use in pregnancy do not indicate an increased risk of major malformations specifically due to buprenorphine. Pregnancy in an opioid dependent woman poses challenges to treating physicians and potential hazards for the fetus including control of illicit drug, nicotine and alcohol use, infections, premature birth, abortion, low birth weight, toxaemia, third trimester bleeding, malpresentation, puerperal morbidity, fetal distress, meconium aspiration, narcotic withdrawal, postnatal growth deficiency, microcephaly, (neuro-) developmental disorders and increased neonatal mortality.

A multicenter, double-blind, double-dummy, flexible-dose study in 175 pregnant women [Maternal Opioid Treatment: Human Experimental Research (MOTHER)] was conducted to study outcomes in neonates born to mothers using methadone or buprenorphine, including the number of neonates requiring treatment for NOWS, the Peak NOWS score, the total amount of morphine needed to treat NOWS, the length of hospital stay for neonates, and neonatal head circumference. The authors found that 18% of pregnant women in the methadone group and 33% in the buprenorphine group discontinued treatment over the course of the pregnancy. They reported no significant difference in the incidence of NOWS, but in the prenatally buprenorphine-exposed condition, the duration of treatment for NOWS was shorter, duration of hospital stays were shorter and the amount of morphine required was significantly less; however, methodological concerns limit the conclusions that may be made.

Animal Data

In an embryofetal development study in rats, SUBLOCADE administered subcutaneously to pregnant animals before mating and again on Gestation Day (GD) 7 during the period of organogenesis resulted in increased post-implantation loss, which correlated with higher mean number of resorptions and decreased number of viable fetuses per litter, and decreased mean fetal body weights at 900 mg/kg (approximately 38 times the maximum recommended human dose [MRHD] of 300 mg of SUBLOCADE on an AUC basis); however, similar effects were observed with an equivalent level of ATRIGEL®delivery system alone, indicating they may be attributable to the vehicle. Dose-related increases in incidences of skeletal malformations of the head and visceral malformations were observed with SUBLOCADE with significant changes at 900 mg/kg (approximately 38 times the MRHD on an AUC basis). Although similar effects were observed with equivalent levels of ATRIGEL®delivery system, the incidence of skeletal malformations, primarily skull malformations, was higher in the SUBLOCADE groups suggesting that buprenorphine contributed to the increased incidence. Based on these results, the NOAEL for developmental toxicity was approximately 15 times the MRHD on an AUC basis.

In an embryofetal development study in rabbits, administration of a single subcutaneous injection of SUBLOCADE to pregnant animals on GD 7 during the period of organogenesis resulted an increased litter incidence of skeletal malformations at 155 mg/kg (approximately 7 times the MRHD on an AUC basis), which appear to be buprenorphine-related adverse effects. There was also an increased litter incidence of external malformations, visceral, and skeletal malformations and variations at 390 mg/kg SUBLOCADE (approximately 15 times the MRHD on an AUC basis); however, similar effects were observed with an equivalent level of the ATRIGEL®delivery system, indicating they may be attributable to the vehicle. In addition, increased post-implantation loss, which correlated with increased mean number of resorptions and decreased mean number of viable fetuses, and decreased fetal body weights were observed at 390 mg/kg (approximately 15 times the MRHD on an AUC basis); however, similar findings were also observed with an equivalent level of the ATRIGEL®delivery system alone. Based on these results, the NOAEL for developmental toxicity for SUBLOCADE was 78 mg/kg (approximately 2 times the MRHD on an AUC basis).

In a pre- and postnatal development study in rats, SUBLOCADE was administered subcutaneously to pregnant animals once during implantation (on GD 7) and once during weaning (on Lactation Day 7). There were no adverse effects on offspring survival, sexual maturation, behavioral assessment, or reproductive performance at up to 300 mg/kg (approximately 15 times the MRHD on an AUC basis).

8.2 Lactation

Risk Summary

Based on two studies in 13 lactating women maintained on buprenorphine treatment, buprenorphine and its metabolite norbuprenorphine are present in low levels in human milk and infant urine. Available data have not shown adverse reactions in breastfed infants. Caution should be exercised when SUBLOCADE is administered to a nursing woman. The developmental and health benefits of breastfeeding should be considered along with the mother's clinical need for SUBLOCADE and any potential adverse effects on the breastfed child from the drug or from the underlying maternal condition.

Clinical Considerations

Advise breastfeeding women taking buprenorphine products to monitor the infant for increased drowsiness and breathing difficulties.

Data

Data were consistent from two studies (N=13) of breastfeeding infants whose mothers were maintained on sublingual doses of buprenorphine ranging from 2.4 to 24 mg/day, showing that the infants were exposed to less than 1% of the maternal daily dose.

In a study of six lactating women who were taking a median sublingual buprenorphine dose of 0.29 mg/kg/day 5 to 8 days after delivery, breast milk provided a median infant dose of 0.42 mcg/kg/day of buprenorphine and 0.33 mcg/kg/day of norbuprenorphine, equal to 0.2% and 0.12%, respectively, of the maternal weight-adjusted dose (relative dose/kg (%) of norbuprenorphine was calculated from the assumption that buprenorphine and norbuprenorphine are equipotent).

Data from a study of seven lactating women who were taking a median sublingual buprenorphine dose of 7 mg/day an average of 1.12 months after delivery indicated that the mean milk concentrations (Cavg) of buprenorphine and norbuprenorphine were 3.65 mcg/L and 1.94 mcg/L respectively. Based on the study data, and assuming milk consumption of 150 mL/kg/day, an exclusively breastfed infant would receive an estimated mean absolute infant dose (AID) of 0.55 mcg/kg/day of buprenorphine and 0.29 mcg/kg/day of norbuprenorphine, or a mean relative infant dose (RID) of 0.38% and 0.18%, respectively, of the maternal weight-adjusted dose.

8.3 Females and Males of Reproductive Potential

Human Data

Chronic use of opioids may cause reduced fertility in females and males of reproductive potential. It is not known whether these effects on fertility are reversible [see Adverse Reactions (6.2)] .

Animal Data

Infertility

Male

Male fertility may be reduced based on animal data demonstrating adverse effects of SUBLOCADE on sperm parameters [see Nonclinical Toxicology (13.1)].

8.4 Pediatric Use

The safety and effectiveness of SUBLOCADE have not been established in pediatric patients.

8.5 Geriatric Use

Clinical studies of SUBLOCADE did not include sufficient numbers of subjects aged 65 and over to determine whether they responded differently than younger subjects. Other reported clinical experience with buprenorphine has not identified differences in responses between geriatric and younger patients.

Due to possible decreased hepatic, renal, or cardiac function and of concomitant disease or other drug therapy in geriatric patients, the decision to prescribe SUBLOCADE should be made cautiously in individuals 65 years of age or older and these patients should be monitored for signs and symptoms of toxicity or overdose.

8.6 Hepatic Impairment

The effect of hepatic impairment on the pharmacokinetics of SUBLOCADE has not been studied.

The effect of hepatic impairment on the pharmacokinetics of sublingual buprenorphine has been evaluated in a pharmacokinetic study. While no clinically significant changes have been observed in subjects with mild hepatic impairment, the plasma levels have been shown to be higher and half-life values have been shown to be longer for buprenorphine in subjects with moderate and severe hepatic impairment.

Because of the long-acting nature of the product, adjustments to dosages of SUBLOCADE are not rapidly reflected in plasma buprenorphine levels. Because buprenorphine levels cannot be rapidly adjusted, patients with pre-existing moderate to severe hepatic impairment are not candidates for treatment with SUBLOCADE.

Patients who develop moderate to severe hepatic impairment while being treated with SUBLOCADE should be monitored for signs and symptoms of toxicity or overdose caused by increased levels of buprenorphine. If signs and symptoms of toxicity or overdose occur within 2 weeks of SUBLOCADE administration, removal of the depot may be required [see Dosage and Administration (2.7), Warnings and Precautions (5.10), Clinical Pharmacology (12.3)] .

8.7 Renal Impairment

Clinical studies of SUBLOCADE did not include subjects with renal impairment. No differences in buprenorphine pharmacokinetics were observed between 9 dialysis-dependent and 6 normal patients following IV administration of 0.3 mg buprenorphine.

9 DRUG ABUSE AND DEPENDENCE

9.1 Controlled Substance

SUBLOCADE contains buprenorphine, a Schedule III substance under the Controlled Substances Act.

9.2 Abuse

SUBLOCADE contains buprenorphine, a Schedule III controlled substance that can be abused similar to other opioids. Patients who continue to misuse, abuse, or divert buprenorphine products or other opioids should be provided with or referred for more intensive and structured treatment. Abuse of buprenorphine poses a risk of overdose and death. This risk is increased with the abuse of buprenorphine and alcohol and other substances, especially benzodiazepines.

SUBLOCADE is distributed through a restricted distribution system, which is intended to prevent the direct distribution to a patient. SUBLOCADE should only be dispensed directly to a healthcare provider for administration by a healthcare provider. It is supplied in prefilled syringes and is intended for administration only by subcutaneous injection by a healthcare provider. The entire contents of the prefilled syringe should be administered. After administration, a small amount (approximately 0.1 mL) of SUBLOCADE will remain in the needle and syringe and should be properly disposed of [see How Supplied/Storage and Handling (16)] .

SUBLOCADE is injected as a liquid, and the subsequent precipitation of the poly (DL-lactide-co-glycolide) polymer creates a solid depot which contains buprenorphine. After initial formation of the depot, buprenorphine is released via diffusion from, and the biodegradation of, the depot. Clinical monitoring for evidence at the injection site of tampering or attempting to remove the depot should be ongoing throughout treatment. No accounts of subjects removing or attempting to remove the depot after administration of SUBLOCADE were reported in premarketing studies.

9.3 Dependence

Buprenorphine is a partial agonist at the mu-opioid receptor and chronic administration produces physical dependence of the opioid type, characterized by moderate withdrawal signs and symptoms upon abrupt discontinuation. The withdrawal syndrome is typically milder than seen with full agonists and may be delayed in onset [see Warnings and Precautions (5.12)] .

Due to the long-acting nature of SUBLOCADE, withdrawal signs and symptoms may not be evident immediately following the discontinuation of treatment.

Neonatal opioid withdrawal syndrome (NOWS) is an expected and treatable outcome of prolonged use of opioids during pregnancy [see Warnings and Precautions (5.7)] .

10 OVERDOSAGE

Clinical Presentation

The manifestations of acute buprenorphine overdose include pinpoint pupils, sedation, hypotension, hypoglycemia, respiratory depression, and death.

Toxic leukoencephalopathy has been reported after opioid overdose and can present hours, days, or weeks after apparent recovery from the initial intoxication.

Treatment of Overdose

In the event of overdose, the respiratory and cardiac status of the patient should be monitored carefully. When respiratory or cardiac functions are depressed, primary attention should be given to the re establishment of adequate respiratory exchange through provision of a patent airway and institution of assisted or controlled ventilation. Oxygen, IV fluids, vasopressors, and other supportive measures should be considered as indicated. An opioid overdose reversal agent may be of value for the management of buprenorphine overdose. Higher than normal doses and repeated administration may be necessary.

Clinicians should consider the potential role and contribution of buprenorphine, other opioids, and other CNS depressant drugs in a patient's clinical presentation. Clinical data are limited with regards to the possible surgical removal of the depot. Two cases of surgical removal were reported in premarketing clinical studies.

11 DESCRIPTION

SUBLOCADE (buprenorphine extended-release) injection is a clear, viscous, colorless to yellow to amber, sterile solution for subcutaneous injection only. It is designed to deliver buprenorphine at a controlled rate over a one month period.

The active ingredient in SUBLOCADE is buprenorphine free base, a mu-opioid receptor partial agonist and a kappa-opioid receptor antagonist.

Buprenorphine is dissolved in the ATRIGEL®delivery system at 18% by weight.

The ATRIGEL®delivery system is a biodegradable 50:50 poly(DL-lactide-co-glycolide) polymer and a biocompatible solvent, N-methyl-2-pyrrolidone (NMP).

SUBLOCADE is provided in dosage strengths of 100 mg and 300 mg. Table 6presents the delivered amounts of the raw materials and the approximate delivered volume for the two dosage strengths.

Table 6 Amounts of Raw Materials and Delivered Volume for the Dosage Strengths
Raw Materials in SUBLOCADE | 100 mg Dosage | 300 mg Dosage
Buprenorphine | 100 mg | 300 mg
Poly(DL-lactide-co-glycolide) | 178 mg | 533 mg
N-methyl-2-pyrrolidone | 278 mg | 833 mg
Approximate Delivered Volume | 0.5 mL | 1.5 mL

The molecular weight of buprenorphine free base is 467.6, and its molecular formula is C29H41NO4. Chemically, buprenorphine is (2S)-2-[17-(Cyclopropylmethyl)-4,5α-epoxy-3-hydroxy-6-methoxy-6α,14-ethano-14α-morphinan-7α-yl]-3,3-dimethylbutan-2-ol. The structural formula is:

12 CLINICAL PHARMACOLOGY

12.1 Mechanism of Action

SUBLOCADE Injection contains buprenorphine. Buprenorphine is a partial agonist at the mu- opioid receptor and an antagonist at the kappa-opioid receptor.

12.2 Pharmacodynamics

Mu-Opioid Receptor Occupancy and Association With Opioid Blockade

In a Positron Emission Tomography (PET) study with SUBLOCADE in 2 subjects (one subject receiving 200 mg subcutaneous injections and one subject receiving 300 mg subcutaneous injections) with opioid use disorder, 75 to 92% occupancy of the mu-opioid receptors in the brain was maintained for 28 days following the last dose under steady-state conditions.

The opioid blockade study evaluated the blockade of subjective opioid effects, pharmacokinetics (PK) and safety of subcutaneous injections of SUBLOCADE. Stabilization doses of SL buprenorphine prior to injection of SUBLOCADE failed to provide full blockade of subjective effects of hydromorphone 18 mg IM. After SUBLOCADE injections at Weeks 0 and 4, on average, subjective effects of both 6 mg and 18 mg doses of hydromorphone were blocked; however, wide variability was seen across subjects. Complete blockade continued throughout the 8 weeks of observation that followed the 2ndSUBLOCADE injection [see Clinical Studies (14.1)] .

Figure 10illustrates the relationship between buprenorphine plasma level and drug liking after 18 mg hydromorphone IM.

Figure 10 Drug Liking VAS vs. Plasma Buprenorphine Concentration Following 18 mg Hydromorphone Challenges

Exposure-response relationships were assessed for illicit opioid use, based on urine samples negative for illicit opioids combined with self-reports negative for illicit opioid use, and withdrawal symptoms using data obtained from 489 opioid dependent patients in the double-blind Phase 3 Study (13-0001).

The observed plateau for maximal response was reached at buprenorphine plasma concentrations of approximately 2-3 ng/mL for illicit opioid use and 4 ng/mL for opioid withdrawal symptoms.

Population PK/PD modeling indicated that patients using opioids by the injectable route at baseline may require higher buprenorphine exposure compared to patients not using opioids by the injectable route at baseline.

Cardiac Electrophysiology

Serial ECGs were collected following a single dose and at steady-state to evaluate the effect of SUBLOCADE on the QT interval in five clinical studies including the Phase 3 study. In a Phase 3 study, seven patients had an increase from baseline QTc greater than 60 msec at any time [2/203 patients (1.0%) in the 300 mg/100 mg group and 5/201 patients (2.0%) in the 300 mg/300 mg group] and one patient in the 300 mg/300 mg group was found to have a QTc greater than 500 msec. These QTc findings were all sporadic and transient and none led to aberrant ventricular rhythm. Review of ECG and adverse event data provided no evidence for syncope, seizure, or ventricular tachycardia or fibrillation.

Physiological Effects

Buprenorphine in IV (2, 4, 8, 12 and 16 mg) and sublingual (12 mg) doses have been administered to opioid-experienced subjects who were not physically dependent to examine cardiovascular, respiratory, and subjective effects at doses comparable to those used for treatment of opioid dependence. Compared to placebo, there were no statistically significant differences among any of the treatment conditions for blood pressure, heart rate, respiratory rate, O2 saturation, or skin temperature across time. Systolic BP was higher in the 8 mg group than placebo (3 hour AUC values). Minimum and maximum effects were similar across all treatments. Subjects remained responsive to low voice and responded to computer prompts. Some subjects showed irritability, but no other changes were observed. The respiratory effects of sublingual buprenorphine were compared with the effects of methadone in a double-blind, parallel group, dose ranging comparison of single doses of buprenorphine sublingual solution (1, 2, 4, 8, 16, or 32 mg) and oral methadone (15, 30, 45, or 60 mg) in non-dependent, opioid-experienced volunteers. In this study, hypoventilation not requiring medical intervention was reported more frequently after buprenorphine doses of 4 mg and higher than after methadone. Both drugs decreased O2 saturation to the same degree.

In clinical studies conducted with SUBLOCADE at doses ranging from 50 to 300 mg, no incidences of temperature elevations, or clinically significant lowering of oxygen saturation were observed.

Androgen Deficiency

Chronic use of opioids may influence the hypothalamic-pituitary-gonadal axis, leading to androgen deficiency that may manifest as low libido, impotence, erectile dysfunction, amenorrhea, or infertility. The causal role of opioids in the clinical syndrome of hypogonadism is unknown because the various medical, physical, lifestyle, and psychological stressors that may influence gonadal hormone levels have not been adequately controlled for in studies conducted to date. Patients presenting with symptoms of androgen deficiency should undergo laboratory evaluation.

Pharmacodynamic Interaction with Fentanyl

An open-label, cross-over study was conducted in 8 opioid-tolerant subjects to assess the ability of intravenous buprenorphine to prevent respiratory depression associated with high doses of fentanyl administered in a clinical setting. Opioid-tolerant subjects were medically stable and taking oral morphine equivalents of ≥ 90 mg daily with no other CNS depressant use. Buprenorphine infusions at three dose levels and placebo infusions were administered, followed by up to four doses of fentanyl. The three intravenous buprenorphine dose levels were designated as low (0.25 mg/70kg bolus + 0.1 mg/70kg/hr), mid (0.5 mg/70kg bolus + 0.2 mg/70kg/hr), and high (1.25 mg/70kg bolus + 0.5 mg/70kg/hr). The low, mid, and high buprenorphine dose levels produced average plasma concentrations (from 2 hours to 6 hours after infusion onset) of 1.06 ng/mL, 2.26 ng/mL, and 6.04 ng/mL, respectively.

Escalating intravenous fentanyl boluses of 0.25, 0.35, 0.50 and 0.70 mg/70 kg (up to a maximum cumulative dose of 1.8 mg/70 kg) were administered over 90 seconds at + 2hr, + 3hr, + 4hr and + 5hr after the start of intravenous infusion of buprenorphine or placebo. Apnea events after each fentanyl bolus are shown in Figure 11. Four of the 8 subjects in the placebo infusion groups discontinued prior to the fourth fentanyl bolus because of apnea (2 after the second bolus and 2 after the third bolus); 3 of the remaining 4 subjects experienced apnea after the fourth fentanyl dose. All 8 subjects in the buprenorphine infusion groups completed the fentanyl boluses and 2 of the 8 experienced apnea.

Figure 11 Occurrence of Apnea Events After Fentanyl Doses in a Pharmacodynamic Interaction Study

There were 2 opioid-tolerant subjects in the low intravenous buprenorphine (BUP) group (Arm A), 3 in the mid BUP group (Arm B), and 3 in the high BUP group (Arm C). The numbers in parentheses represent the geometric mean of buprenorphine plasma concentrations in each group from 2 hours to 6 hours after infusion onset. The escalating fentanyl doses 1 to 4 were 0.25, 0.35, 0.50 and 0.70 mg/70 kg body weight. The same subject in the low BUP group had apnea after the third and fourth fentanyl boluses.

12.3 Pharmacokinetics

Absorption

The pharmacokinetics (PK) of buprenorphine following subcutaneous injection of SUBLOCADE was evaluated in subjects with opioid use disorder after single doses (50 mg to 200 mg) and repeated doses (50 to 300 mg) separated by 28 days for up to 12 injections.

After SUBLOCADE injection, an initial buprenorphine peak was observed and the median Tmax occurred at 24 hours after injection. After the initial buprenorphine peak, the plasma buprenorphine concentrations decreased slowly to a plateau. Steady-state was achieved at 4-6 months.

Mean buprenorphine plasma concentrations levels for Cavg, Cmax and Ctrough at steady-state are presented in Table 7for SUBLOCADE in comparison to daily transmucosal buprenorphine.

Table 7 Comparison of Steady-state Buprenorphine Plasma Exposure Between Daily Transmucosal Buprenorphine and Once Monthly SUBLOCADE at Trough (Ctrough), Average (Cavg) and Peak (Cmax) Levels (Geometric Mean (CV%))
Pharmacokinetic parameters | Transmucosal Buprenorphine |  |  |  | SUBLOCADE
Pharmacokinetic parameters | 8 mg | 12 mg | 16 mg | 24 mg | 100 mg | 300 mg
Cavg,ss(ng/mL) | 1.37 (40) | 1.79 (40) | 2.16 (40) | 2.84 (40) | 2.87 (32) | 6.32 (32)
Cmax,ss(ng/mL) | 4.27 (45) | 5.60 (45) | 6.77 (45) | 8.86 (45) | 5.10 (33) | 11.81 (35)
Ctrough,ss(ng/mL) | 0.66 (63) | 0.87 (63) | 1.04 (61) | 1.37 (62) | 2.46 (40) | 5.47 (39)

At steady state, buprenorphine plasma concentrations achieved with 100 mg monthly dosing are contained within the range obtained with transmucosal treatment; peak concentrations with SUBLOCADE may be lower, while average and trough concentrations may be higher. Potential differences in steady state levels need to be taken into consideration when transitioning a patient established on long term treatment with transmucosal buprenorphine to SUBLOCADE.

Distribution

Buprenorphine is approximately 96% protein bound, primarily to alpha and beta globulin.

Elimination

Buprenorphine is metabolized and eliminated in urine and feces. The apparent terminal plasma half-life of buprenorphine following subcutaneous injection of SUBLOCADE ranged between 43 to 60 days as a result of the slow release of buprenorphine from the subcutaneous depot.

A study assessing buprenorphine exposure 22 to 38 months following the last SUBLOCADE injection indicated that buprenorphine could potentially be detected in plasma and urine over that time period. Concentrations in urine were more variable than in plasma and generally higher depending on the test used. Hence, it is expected that buprenorphine will be detected in patients for a longer time in urine than in plasma.

Metabolism

Buprenorphine is metabolized to its major metabolite, norbuprenorphine, primarily by CYP3A4. Norbuprenorphine can further undergo glucuronidation. Norbuprenorphine has been found to bind opioid receptors in vitro; however, it has not been studied clinically for opioid-like activity. Norbuprenorphine steady-state plasma concentrations in humans after subcutaneous injection of SUBLOCADE are low compared to buprenorphine (AUC norbuprenorphine/buprenorphine ratio of 0.20 to 0.40).

Excretion

A mass balance study of buprenorphine administered by IV infusion in humans showed complete recovery of radiolabel in urine (30%) and feces (69%) collected up to 11 days after dosing. Almost all of the dose was accounted for in terms of buprenorphine, norbuprenorphine, and two unidentified buprenorphine metabolites. In urine, most of buprenorphine and norbuprenorphine were conjugated (buprenorphine: 1% free and 9.4% conjugated; norbuprenorphine: 2.7% free and 11% conjugated). In feces, almost all of the buprenorphine and norbuprenorphine were free (buprenorphine: 33% free and 5% conjugated; norbuprenorphine: 21% free and 2% conjugated).

Drug Interaction Studies

CYP3A4 Inhibitors and Inducers

The effects of co-administered CYP3A4 inhibitors and inducers on buprenorphine exposure in subjects treated with SUBLOCADE have not been studied; however, such interactions have been established in studies using transmucosal buprenorphine. The effects of buprenorphine may be dependent on the route of administration.

Buprenorphine is metabolized to norbuprenorphine primarily by cytochrome CYP3A4; therefore, potential interactions may occur when SUBLOCADE is given concurrently with agents that affect CYP3A4 activity. The effects of co-administered CYP3A4 inducers or inhibitors have been established in studies using transmucosal buprenorphine. Patients who transfer to SUBLOCADE treatment from a regimen of transmucosal buprenorphine used concomitantly with CYP3A4 inhibitors (e.g., ketoconazole), macrolide antibiotics (e.g., erythromycin), or HIV protease inhibitors, or CYP3A4 inducer (e.g., phenobarbital, carbamazepine, phenytoin, rifampicin) should be monitored to ensure that the plasma buprenorphine level provided by SUBLOCADE is adequate and not excessive [see Drug Interactions (7)].

Buprenorphine has been found to be a CYP2D6 and CYP3A4 inhibitor and its major metabolite, norbuprenorphine, has been found to be a moderate CYP2D6 inhibitor in in vitro studies employing human liver microsomes. However, the plasma concentrations of buprenorphine and norbuprenorphine resulting from therapeutic SUBLOCADE doses are not expected to significantly affect metabolism of other co-medications.

Specific Populations

Based on population pharmacokinetic analyses, age, sex, and race do not have a clinically meaningful effect on PK of SUBLOCADE.

Hepatic Impairment

The effect of hepatic impairment on the pharmacokinetics of SUBLOCADE has not been studied. However, the effect of hepatic impairment on the PK of buprenorphine has been evaluated in a study using 2 mg/0.5 mg buprenorphine/naloxone sublingual tablet in subjects with various degrees of hepatic impairment as indicated by Child-Pugh criteria. While no clinically relevant changes were observed in subjects with mild hepatic impairment, buprenorphine plasma exposure was increased by 64% and 181% in subjects with moderate and severe hepatic impairment, respectively, compared to healthy subjects [see Use in Specific Populations (8.6)] .

Renal Impairment

The effect of renal impairment on the pharmacokinetics of SUBLOCADE has not been studied. Clinical studies of SUBLOCADE did not include subjects with severe renal impairment.

Less than 1% is excreted as unchanged buprenorphine in urine following IV buprenorphine administration. No differences in buprenorphine pharmacokinetics were observed between 9 dialysis-dependent and 6 normal patients following IV administration of 0.3 mg buprenorphine [see Use in Specific Populations (8.7)] .

Population PK analyses indicated no notable relationship between creatinine clearance and steady-state buprenorphine plasma concentrations.

HCV infection

In subjects with HCV infection but no sign of hepatic impairment, the changes in the mean Cmax, AUC0-last, and half-life values of buprenorphine were not clinically significant in comparison to healthy subjects without HCV infection. No dose adjustment is needed in patients with HCV infection.

13 NONCLINICAL TOXICOLOGY

13.1 Carcinogenesis, Mutagenesis, Impairment of Fertility

Carcinogenicity

Long-term studies in animals performed to evaluate carcinogenic potential of SUBLOCADE have not been conducted. However, the carcinogenic potential of the active drug substance in SUBLOCADE, buprenorphine, has been evaluated in Sprague-Dawley rats and CD-1 mice.

In the carcinogenicity study conducted in Sprague-Dawley rats, buprenorphine was administered in the diet at doses of 0.6, 5.5, and 56 mg/kg/day (approximately 0.5, 5, and 50 times the recommended human monthly subcutaneous dose of 300 mg of buprenorphine) for 27 months. A statistically significant dose-related increase in Leydig cell tumors occurred. In an 86 week study in CD-1 mice, buprenorphine was not carcinogenic at dietary doses up to 100 mg/kg/day (approximately 45 times the recommended human monthly subcutaneous dose of 300 mg of buprenorphine).

N-methyl-2-pyrrolidone [NMP], an excipient in SUBLOCADE, produced an increase in hepatocellular adenomas and carcinomas in male and female mice at 6 and 8 times the maximum daily dose (MDD) of NMP via SUBLOCADE. The clinical significance of these findings is unclear. No tumors were noted at 1 and 1.3 times the MDD. In 2-year inhalation and dietary studies in rats, NMP did not result in evidence of carcinogenicity.

Mutagenicity

No evidence of mutagenic potential for subcutaneous SUBLOCADE was found in in vivo subcutaneous micronucleus test using rats' marrow.

Mutagenic potential for buprenorphine was studied in a series of tests utilizing gene, chromosome, and DNA interactions in both prokaryotic and eukaryotic systems. Results were negative in yeast (S. cerevisiae) for recombinant, gene convertant, or forward mutations; negative in Bacillus subtilis “rec” assay, negative for clastogenicity in CHO cells, Chinese hamster bone marrow and spermatogonia cells, and negative in the mouse lymphoma L5178Y assay.

Results were equivocal in the Ames test: negative in studies in two laboratories, but positive for frame shift mutation at a high dose (5 mg/plate) in a third study. Results were positive in the Green-Tweets (E. coli) survival test, positive in a DNA synthesis inhibition (DSI) test with testicular tissue from mice, for both in vivoand in vitroincorporation of [3H]thymidine, and positive in unscheduled DNA synthesis test using testicular cells from mice.

Impairment of Fertility

In a fertility study in rats, SUBLOCADE or ATRIGEL®was administered every 28 days for 3 months (males) or once before mating and once on GD 7; female mating, fertility, and fecundity indices were unaffected by the subcutaneous administration of SUBLOCADE up to 900 mg/kg buprenorphine (approximately 38 times the maximum recommended human dose [MRHD] of 300 mg on an AUC basis). However, higher mean post-implantation loss was observed with SUBLOCADE at 900 mg/kg buprenorphine and at an equivalent level of ATRIGEL®alone, which correlated with higher mean number of resorptions and reduced mean number of viable fetuses/litter size. Mean gravid uterine weight and mean final body weight were lower with SUBLOCADE at 900 mg/kg buprenorphine and an equivalent level of the ATRIGEL®alone, and correlated with higher mean number of resorptions and lower fetal body weights. The NOAEL for female fertility was 900 mg/kg and the NOAEL for female-mediated developmental parameters was 600 mg/kg (approximately 25 times the MRHD on an AUC basis).

Male fertility and reproduction indices were lower as evidenced by abnormal sperm parameters (low motility, low mean number of sperm, and higher percentage of abnormal sperm) with SUBLOCADE at 600 mg/kg and with an equivalent level of ATRIGEL®. The NOAEL for male fertility parameters, including sperm analysis, and male-mediated developmental parameters was 300 mg/kg (approximately 32 times the MRHD on an AUC basis).

14 CLINICAL STUDIES

The key studies from the SUBLOCADE clinical development program that support its use in moderate to severe OUD are a Phase 3 double-blind efficacy and safety study (13-0001, NCT02357901), an opioid blockade study (13-0002, NCT02044094), and a study evaluating rapid induction of SUBLOCADE after an initial dose of transmucosal buprenorphine (Rapid Induction Substudy INDV-6000-401, NCT04995029).

14.1 Study 13-0002, NCT02044094

The opioid blockade study evaluated the blockade of subjective opioid effects, PK and safety of subcutaneous injections of SUBLOCADE in 39 subjects with OUD (not treatment-seeking).

The peak (Emax) effect of “Drug Liking” Visual Analog Scale (VAS) measurement after challenge with IM injections of 6 mg and 18 mg hydromorphone (HM) was not inferior (i.e., shown to be not substantially more likeable) compared to the Emax of “Drug Liking” VAS measured after challenge with placebo (at weeks 1 through 4 following the first injection of 300 mg SUBLOCADE). The noninferiority (NI) margin, the largest difference allowed for the 6 or 18 mg HM VAS to exceed the placebo VAS (the maximum VAS recorded following IM injection of 0 mg HM) before being considered significant, was set at 20. Based on comparison to the historical response to opioid agonists in unblocked subjects, a difference of less than 20 points (on a unipolar scale) between the mean maximum response to hydromorphone and the mean maximum placebo response for the same challenge was considered to indicate near-complete blockade.

All 12 weeks of the treatment period demonstrated blockade for both 6 mg and 18 mg following SUBLOCADE injections. However, wide variation can be seen in isolated measurements from individual subjects, shown in the figure below. For comparison, stabilization doses of SL buprenorphine in Week 0 failed to provide full blockade to 18 mg of HM. Complete blockade continued throughout the 8 weeks of observation that followed the 2ndSUBLOCADE injection.

Figure 12 Median (95% Confidence Interval) of Placebo-Corrected Drug-Liking Scores by Hydromorphone Dose and by Week

- Key to Figure: The grey shaded area indicates the period where subjects were stabilized with 8 to 24 mg/day sublingual (SL) buprenorphine; the two vertical arrows represent treatment injections of SUBLOCADE, with 300 mg of buprenorphine.
- The light grey and dark grey squares represent the median Emax drug-liking scores, placebo-corrected (VAS drug liking for that week's 0 mg dose subtracted) during the hydromorphone challenge of 6 and 18 mg, respectively. This median Placebo-Corrected Emax is shown by treatment week, together with its 95% confidence interval (CI; vertical line). In some cases, 95% CI are not visible as the median was equal to the confidence limit. The horizontal line at 20 mm delineates the non-inferiority margin for opioid blockade. Next to median estimates, individual data are summarized by circles, the area of which is proportional to the number of subjects at that location.
- The X axis shows how many weeks following injection #1 that each weeks' Placebo-Corrected Drug-Liking Score was measured. Beneath that treatment week indicator, is the number of subjects (N) who provided those VAS measurements for all three challenges with placebo, 6 and 18 mg hydromorphone.

14.2 Study 13-0001, NCT02357901

The efficacy of SUBLOCADE for the treatment of opioid use disorder was evaluated in a Phase 3, 24- week, randomized, double-blind, placebo-controlled, multicenter trial in treatment-seeking patients who met the DSM-5 criteria for moderate or severe opioid use disorder. Patients were randomized to one of following dosing regimens: 6 once-monthly 300 mg doses, 2 once-monthly 300 mg doses followed by 4 once-monthly 100 mg doses, or 6 once-monthly subcutaneous injections of placebo. All doses were administered by a physician or suitably qualified designee and were separated by 28 ± 2 days. In addition to study medication, all subjects received manual-guided psychosocial support at least once a week (Individual Drug Counseling = IDC).

Prior to the first dose, treatment was initiated with SUBOXONE®(buprenorphine/naloxone) sublingual film (SUBOXONE SL Film); doses were adjusted from 8/2 mg to 24/6 mg per day over a period of 7-14 days. Patients were randomized to SUBLOCADE injection or placebo after cravings and withdrawal symptoms were clinically controlled. After randomization, supplemental dosing with SUBOXONE SL Film was not permitted during the study.

Efficacy was evaluated over Weeks 5 through 24 based on weekly urine drug screens combined with self-reported use of illicit opioid use. A “grace period” was applied for Weeks 1 through 4 to allow patients to stabilize in treatment. During this period, opioid use, if it occurred, was not considered in the analysis. Missing urine drug screen samples and/or self-reports during Weeks 5-24 were counted as positive for illicit opioids.

A total of 504 patients were randomized 4:4:1:1 [203 subjects in the 300 mg/100 mg group, 201 patients in the 300 mg/300 mg group and 100 patients in the placebo group (2 groups of volume-matched placebo)]. Patient demographics and baseline characteristics are provided in Table 8.

Table 8 Patient Demographics and Baseline Characteristics
 | SUBLOCADE 300/100 mg % (N = 194) | SUBLOCADE 300/300 mg % (N = 196) | Placebo % (N = 99)
Mean Age (years) | 40.4 | 39.3 | 39.2
Sex
Male | 66.0 | 67.3 | 64.6
Female | 34.0 | 32.7 | 35.4
Race or Ethnicity
White | 68.0 | 71.4 | 77.8
Black or African American | 28.9 | 27.6 | 20.2
Hispanic or Latino | 6.2 | 9.2 | 10.1
Substance Use At Screening
Opioid Use - Injectable Route | 43.3 | 40.8 | 50.5
Tobacco | 91.8 | 92.3 | 92.9
Alcohol | 78.4 | 79.1 | 80.8
Drug Use History
Cannabinoids | 54.6 | 47.4 | 52.5
Cocaine | 47.4 | 39.8 | 42.4
Amphetamine/Methamphetamine | 25.3 | 14.8 | 19.2
Medical History
Depression | 14.4 | 11.2 | 13.1
Anxiety | 9.3 | 9.7 | 10.1
Back Pain | 14.9 | 16.3 | 13.1

Based on the cumulative distribution function (CDF) of the percentage of urine samples negative for illicit opioids combined with self-reports negative for illicit opioid use collected from Week 5 through Week 24 (Table 9), regardless of dose, SUBLOCADE was superior to the placebo group with statistical significance. The proportion of patients achieving treatment success (defined as patients with ≥ 80% opioid-free weeks) was statistically significantly higher in both groups receiving SUBLOCADE compared to the placebo group (28.4% [300 mg/100 mg], 29.1% [300 mg/300mg], 2% [placebo]).

For various percentages of opioid-free weeks, Table 9shows the fraction of patients achieving that criterion. The table is cumulative, so that a patient whose percent of opioid-free weeks is, for example, 50%, is also included at every level of opioid-free week percentage below 50%. Missing values and values after premature discontinuation were considered positive.

Figure 13 Subjects Achieving Varying Percentages of Opioid-Free Weeks

Table 9 Cumulative Distribution Function of Percentage of Opioid-Free Weeks
 | Number (%) of Subjects
 | SUBLOCADE | SUBLOCADE
 | 300 mg/100 mg + IDC | 300 mg/300 mg + IDC | Placebo + IDC
Percentage Opioid-Free Weeks | (N = 194) | (N = 196) | (N = 99)
≥ 0% | 194 (100.0) | 196 (100.0) | 99 (100.0)
≥ 10% | 139 (71.6) | 126 (64.3) | 11 (11.1)
≥ 20% | 115 (59.3) | 111 (56.6) | 7 (7.1)
≥ 30% | 101 (52.1) | 101 (51.5) | 6 (6.1)
≥ 40% | 90 (46.4) | 90 (45.9) | 6 (6.1)
≥ 50% | 86 (44.3) | 82 (41.8) | 4 (4.0)
≥ 60% | 78 (40.2) | 70 (35.7) | 4 (4.0)
≥ 70% | 66 (34.0) | 67 (34.2) | 2 (2.0)
≥ 80% | 55 (28.4) | 57 (29.1) | 2 (2.0)
≥ 90% | 41 (21.1) | 48 (24.5) | 2 (2.0)
= 100% | 25 (13) | 23 (12) | 1 (1.0)

14.3 Rapid Induction Substudy INDV-6000-401, NCT04995029

Induction on SUBLOCADE following a single dose of 4 mg transmucosal buprenorphine was compared to standard induction (minimum of 7 days of transmucosal buprenorphine) based on data from 723 treatment-seeking patients with moderate to severe OUD and high-risk opioid use. High-risk opioid use was defined as using five or more days per week either via IV injection, high doses (at least 500 mg IV heroin equivalent), or potent synthetic opioids (e.g., fentanyl). At induction, 77.5% of patients were fentanyl positive by urine drug screen (UDS).

In this open-label study, patients were randomized at a 2:1 ratio to SUBLOCADE rapid induction or standard induction and stratified according to the same-day UDS result for fentanyl due to the potential for fentanyl use to impact the response to induction. For rapid induction, patients were observed at a minimum of 1 hour after receiving a single dose of 4 mg transmucosal buprenorphine to confirm tolerability before administering the first injection of 300 mg SUBLOCADE. On induction day, up to an additional 8 mg of transmucosal buprenorphine could be administered to manage withdrawal symptoms. In both treatment groups, the second 300 mg injection was administered at 1 week after the first SUBLOCADE injection and subsequent injections were scheduled every 4 weeks.

Rapid induction was effective, shown by the primary endpoint of participant retention at the second injection. The proportion of participants who received the second injection was 66.4% in the rapid induction arm and 54.5% in the standard induction arm; the estimated retention rate difference (rapid induction minus standard induction) in the overall population was 11.8% with a lower bound of multiplicity adjusted two-sided 95% confidence interval greater than the pre-specified non-inferiority margin of -10%. This demonstrated non-inferiority of rapid induction to standard induction.

16 HOW SUPPLIED/STORAGE AND HANDLING

SUBLOCADE injection is available as a sterile, clear, viscous, colorless to yellow to amber solution in a single dose, prefilled syringe with safety needle.

SUBLOCADE, 100 mg/0.5 mL – NDC 12496-0100-1

SUBLOCADE, 300 mg/1.5 mL – NDC 12496-0300-1

Storage and Handling

Store refrigerated at 2°C to 8°C (35.6°F to 46.4°F).

Once outside the refrigerator this product may be stored in its original packaging at room temperature, 15°C to 30°C (59°F to 86°F), for up to 12 weeks prior to administration. Discard SUBLOCADE if left at room temperature for longer than 12 weeks.

SUBLOCADE is a Schedule III drug product. Handle with adequate security and accountability. After administration, syringes should be properly disposed, per facility procedure for a Schedule III drug product, and per applicable federal, state, and local regulations.

Rx Only.

17 PATIENT COUNSELING INFORMATION

Advise the patient to read the FDA-approved patient labeling (Medication Guide).

SUBLOCADE Risk Evaluation and Mitigation Strategy (REMS)

Advise patients that because of the risk of serious harm or death due to intravenous self-administration, SUBLOCADE is available only through a restricted program called the SUBLOCADE REMS Program. Healthcare settings and pharmacies are certified and only dispense SUBLOCADE directly to a healthcare provider for administration by healthcare providers [see Warnings and Precautions (5.2)] .

Life Threatening Respiratory Depression

Educate patients and caregivers on how to recognize respiratory depression and emphasize the importance of calling 911 or getting emergency medical help right away in the event of a known or suspected overdose [see Warnings and Precautions 5.4)] .

Patient Access to an Opioid Overdose Reversal Agent for the Emergency Treatment of Opioid Overdose

Inform patients and caregivers about opioid overdose reversal agents (e.g., naloxone, nalmefene) and discuss the importance of having access to an opioid overdose reversal agent. Because patients being treated for opioid use disorder are at risk for relapse, discuss the importance of having access to an opioid overdose reversal agent. Also discuss the importance of having access to an opioid overdose reversal agent if there are household members (including children) or other close contacts at risk for accidental ingestion or opioid overdose.

Discuss with the patient the options for obtaining an opioid overdose reversal agent (e.g., prescription, over-the-counter (some products), or as part of a community-based program) [see Dosage and Administration (2.2), Warnings and Precautions (5.4)].

There are important differences among the opioid overdose reversal agents. Be familiar with these differences, as outlined in the approved labeling for those products, prior to recommending or prescribing such an agent.

Educate patients and caregivers on how to recognize the signs and symptoms of an opioid overdose.

Explain to patients and caregivers that effects of opioid overdose reversal agents like naloxone and nalmefene are temporary, and that they must call 911 or get emergency medical help right away in all cases of known or suspected opioid overdose, even if an opioid overdose reversal agent is administered. Repeat administration may be necessary, particularly for overdose involving buprenorphine [see Dosage and Administration (2.2), Warnings and Precautions (5.4), Overdosage (10)] .

Advise patients and caregivers:

- how to treat with an opioid overdose reversal agent in the event of an opioid overdose
- to tell family and friends about their opioid overdose reversal agent, and to keep it in a place where family and friends can easily access it in an emergency
- to read the Patient Information (or other educational material) that will come with their opioid overdose reversal agent. Emphasize the importance of doing this before an opioid emergency happens, so the patient and caregiver will know what to do

Interaction With Benzodiazepines and Other CNS Depressants

Inform patients and caregivers that potentially fatal additive effects may occur if SUBLOCADE is used with benzodiazepines or other CNS depressants (e.g., alcohol, non-benzodiazepine sedative/hypnotics, anxiolytics, tranquilizers, muscle relaxants, general anesthetics, antipsychotics, gabapentinoids [gabapentin or pregabalin], and other opioids) and not to use these concomitantly unless supervised by a healthcare provider [see Warnings and Precautions (5.4, 5.5), Drug Interactions (7)].

Serotonin Syndrome

Inform patients that SUBLOCADE could cause a rare but potentially life-threatening condition resulting from concomitant administration of serotonergic drugs. Warn patients of the symptoms of serotonin syndrome and to seek medical attention right away if symptoms develop. Instruct patients to inform their healthcare providers if they are taking, or plan to take serotonergic medications [see Drug Interactions (7)].

Adrenal Insufficiency

Inform patients that SUBLOCADE could cause adrenal insufficiency, a potentially life-threatening condition. Adrenal insufficiency may present with non-specific symptoms and signs such as nausea, vomiting, anorexia, fatigue, weakness, dizziness, and low blood pressure. Advise patients to seek medical attention if they experience a constellation of these symptoms [see Warnings and Precautions (5.8)].

Anaphylaxis

Inform patients that anaphylaxis has been reported with buprenorphine. Advise patients how to recognize such a reaction and when to seek medical attention [see Warnings and Precautions (5.11)].

Driving or Operating Heavy Machinery

Caution patients that SUBLOCADE may impair the mental or physical abilities required for the performance of potentially dangerous tasks such as driving or operating hazardous machinery. Instruct patients not to drive or operate hazardous machinery until they are reasonably certain that SUBLOCADE does not adversely affect their ability to engage in such activities [see Warnings and Precautions (5.17)] .

Dependence and Withdrawal

Inform patients that SUBLOCADE can cause drug dependence and that withdrawal signs and symptoms may occur when the medication is discontinued [see Warnings and Precautions (5.9, 5.12)].

Orthostatic Hypotension

Inform patients that, like other opioids, SUBLOCADE may produce orthostatic hypotension in ambulatory individuals [see Warnings and Precautions (5.18)].

Long Duration of Action

Inform patients that they may have detectable levels of buprenorphine for a prolonged period of time after treatment with SUBLOCADE. Considerations of drug-drug interactions, buprenorphine effects, and analgesia may continue to be relevant for several months after the last injection [see Clinical Pharmacology (12.3)] .

Drug Interactions

Instruct patients to inform their healthcare providers of any other prescription medications, over the-counter medications, or herbal preparations that are prescribed or currently being used [see Drug Interactions (7)].

Pregnancy

Neonatal Opioid Withdrawal Syndrome

Advise women that if they are pregnant while being treated with SUBLOCADE, the baby may have signs of withdrawal at birth and that withdrawal is treatable [see Warnings and Precautions (5.6), Use in Specific Populations (8.1)].

Embryofetal Toxicity

Advise women of childbearing potential who become pregnant or are planning to become pregnant to consult their healthcare provider regarding the possible effects of using SUBLOCADE during pregnancy [see Use in Specific Populations (8.1)].

Lactation

Warn patients that buprenorphine passes into breast milk. Advise the nursing mother taking buprenorphine to monitor the infant for increased drowsiness and breathing difficulties [see Use in Specific Populations (8.2)].

Infertility

Inform patients that chronic use of opioids may cause reduced fertility. It is not known whether these effects on fertility are reversible [see Use in Specific Populations (8.3), Clinical Pharmacology (12.2)].

Emergency Analgesia

Patients should be advised to instruct their family members to, in the event of emergency, inform the treating healthcare provider or emergency room staff that the patient is physically dependent on an opioid and that the patient is being treated with SUBLOCADE [see Warnings and Precautions (5.13)] .

Clinical Monitoring

Tell your patients to seek emergency attention if they have signs or symptoms of respiratory or CNS depression or overdose [see Warnings and Precautions (5.4, 5.5)] .

Tell your patients not to tamper with or try to remove their depot [see Dosage and Administration (2.7)].

© 2025 Indivior UK Limited | SUBLOCADE® is a registered trademark of Indivior UK Limited or its affiliate companies. | All rights reserved. All third-party trademarks used herein are registered trademarks of their respective owner(s).

Manufactured for Indivior Inc., North Chesterfield VA, 23235

MEDICATION GUIDE
SUBLOCADE (SUB-lo-kade) (buprenorphine extended-release) injection, for subcutaneous use, (CIII)

What is the most important information I should know about SUBLOCADE?

- Because of the serious risk of potential harm or death from self-injecting SUBLOCADE into a vein (intravenously), it is only available through a restricted program called the SUBLOCADE REMS Program.
  - SUBLOCADE is not available in retail pharmacies.
  - Your SUBLOCADE injection will only be given to you by a certified healthcare provider.
- SUBLOCADE contains a medicine called buprenorphine. Buprenorphine is an opioid that can cause serious and life-threatening breathing problems, especially if you take or use certain other medicines or drugs.
- Ask your healthcare provider about medicines like naloxone or nalmefene that can be used in an emergency to reverse opioid overdose. If naloxone or nalmefene is given, you must call 911 or get emergency medical help right away to treat overdose or accidental use of an opioid.
- SUBLOCADE may cause serious and life-threatening breathing problems. Get emergency medical help right away if you:
  - feel faint
  - feel dizzy
  - are confused
  - feel sleepy or uncoordinated
  - have blurred vision
  - have slurred speech
  - are breathing slower than normal
  - cannot think well or clearly
- Do not take SUBLOCADE with certain medicines. Taking SUBLOCADE with other opioid medicines, benzodiazepines, gabapentinoids (gabapentin or pregabalin), alcohol, or other central nervous system depressants (including street drugs) can cause severe drowsiness, decreased awareness, breathing problems, coma, and death.
- In an emergency, have family members tell emergency department staff that you are physically dependent on an opioid and are being treated with SUBLOCADE.
- You may have detectable levels of SUBLOCADE in your body for several months after stopping treatment with SUBLOCADE.

What is SUBLOCADE?
SUBLOCADE is a prescription medicine used to treat adults with moderate to severe addiction (dependence) to opioid drugs (prescription or illegal) who:

- have started treatment with a single dose of a buprenorphine medicine in the form of a sublingual tablet or buccal film (transmucosal) or
- are already being treated with buprenorphine.

SUBLOCADE is part of a complete treatment plan that should include counseling and psychosocial support.

Who should not receive SUBLOCADE?
Do not receive SUBLOCADE if you are allergic to buprenorphine or any ingredients in the prefilled syringe (ATRIGEL® delivery system). See the end of this Medication Guide for a list of ingredients in SUBLOCADE.

Before receiving SUBLOCADE, tell your healthcare provider about all your medical conditions, including if you have:

- trouble breathing or lung problems
- a curve in your spine that affects your breathing
- Addison's disease

- an enlarged prostate (men)
- problems urinating
- liver, kidney, or gallbladder problems
- alcoholism

- a head injury or brain problem
- mental health problems
- adrenal gland or thyroid gland problems

Tell your healthcare provider if you are:

- pregnant or plan to become pregnant. If you receive SUBLOCADE while pregnant, your baby may have symptoms of opioid withdrawal at birth that could be life-threatening if not recognized and treated. Talk to your healthcare provider if you are pregnant or plan to become pregnant.
- breastfeeding or plan to breastfeed. SUBLOCADE can pass into your breast milk and harm your baby. Talk to your healthcare provider about the best way to feed your baby during treatment with SUBLOCADE. Monitor your baby for increased drowsiness and breathing problems if you breastfeed during treatment with SUBLOCADE.

Tell your healthcare provider about all the medicines you take, including prescription and over-the-counter medicines, vitamins and herbal supplements. Talk with your healthcare provider before starting any new medicines during or after stopping treatment with SUBLOCADE.

How will I receive SUBLOCADE?

- You will receive SUBLOCADE by your healthcare provider as an injection just under the skin (subcutaneous) of your stomach (abdomen), thigh, buttock, or back of the upper arm. After the first two injections, you will receive SUBLOCADE monthly (with at least 26 days between doses).
- If you are not currently receiving buprenorphine treatment, your healthcare provider will give you a test dose of buprenorphine first to see if you are able to tolerate it, before switching to SUBLOCADE.
- SUBLOCADE is injected as a liquid. After the injection, SUBLOCADE changes to a solid form called a depot. The depot may be seen or felt as a small bump under your skin at the injection site for several weeks. The depot will get smaller over time.
- Do not try to remove the depot.
- Do not rub or massage the injection site.
- Try not to let any restrictive clothing such as belts, waistbands, or sleeves rub against the injection site.
- If you miss a dose of SUBLOCADE, see your healthcare provider to get your SUBLOCADE injection as soon as possible.

What should I avoid while being treated with SUBLOCADE?

- Do not drive, operate heavy machinery, or perform any other dangerous activities until you know how SUBLOCADE affects you. SUBLOCADE can cause drowsiness and slow reaction times. SUBLOCADE can make you sleepy, dizzy, or lightheaded. This may happen more often in the first few days after your injection and when your dose is changed.
- You should not drink alcohol or take prescription or over-the-counter medicines that contain alcohol during treatment with SUBLOCADE, because this can lead to loss of consciousness or even death.

What are the possible side effects of SUBLOCADE?
SUBLOCADE can cause serious side effects, including:

- Trouble breathing. Taking SUBLOCADE with other opioid medicines, benzodiazepines, gabapentinoids (gabapentin or pregabalin), alcohol, or other central nervous system depressants (including street drugs) can cause breathing problems that can lead to coma and death.
- Sleepiness, dizziness, and problems with coordination.
- Physical dependence or abuse.
- Liver problems. Call your healthcare provider right away if you notice any of these symptoms:
  - your skin or the white part of your eyes turns yellow (jaundice)
  - dark or “tea-colored” urine
  - light colored stools (bowel movements)
  - loss of appetite
  - pain, aching, or tenderness on the right side of your stomach area
  - nausea
  Your healthcare provider should do blood tests to check your liver before you start and during treatment with SUBLOCADE.
- Allergic reaction. You may have a rash, hives, swelling of your face, wheezing, light-headedness, feeling faint or loss of consciousness. Call your healthcare provider or get emergency help right away.
- Opioid withdrawal. Call your healthcare provider right away if you get any of these symptoms:
  - shaking
  - sweating more than normal
  - feeling hot or cold more than normal
  - runny nose
  - watery eyes
  - goose bumps
  - diarrhea
  - vomiting
  - muscle aches
- Decrease in blood pressure. You may feel dizzy when you get up from sitting or lying down.

The most common side effects of SUBLOCADE include:

- constipation
- headache
- nausea
- injection site itching

- vomiting
- increase in liver enzymes
- tiredness
- injection site pain

SUBLOCADE may affect fertility in males and females. Talk to your healthcare provider if this is a concern for you.
These are not all the possible side effects of SUBLOCADE.
Call your doctor for medical advice about side effects. You may report side effects to the FDA at 1-800-FDA-1088.

General information about SUBLOCADE
Medicines are sometimes prescribed for purposes other than those listed in a Medication Guide. You can ask your doctor or pharmacist for information that is written for healthcare professionals.

What are the ingredients in SUBLOCADE?
Active ingredient: buprenorphine
ATRIGEL®Delivery system: biodegradable 50:50 poly(DL-lactide-co-glycolide) polymer and a biocompatible solvent, N-methyl-2-pyrrolidone (NMP).

© 2025 Indivior UK Limited | SUBLOCADE® is a registered trademark of Indivior UK Limited or its affiliate companies. | All rights reserved. All third-party trademarks used herein are registered trademarks of their respective owner(s).
Manufactured for Indivior Inc., North Chesterfield VA, 23235
For more information, go to www.SUBLOCADE.com or call 1-877-782-6966.

This Medication Guide has been approved by the U.S. Food and Drug Administration. Revised: 12/2025

Principal Display Panel - Sublocade 100 mg Carton Label

NDC 12496-0100-1

Sublocade ®

(buprenorphine extended-release)
injection

CIII

100 mg

FOR SUBCUTANEOUS USE ONLY

WARNING: SERIOUS HARM OR DEATH
COULD RESULT IF INJECTED INTRAVENOUSLY

To be administered by a healthcare provider only.

CARTON CONTENTS: One pouch with sterile prefilled syringe containing
100 mg/0.5 mL of buprenorphine in the ATRIGEL® Delivery System, one
oxygen absorber and one sterile 19 G 5/8" safety needle.

Principal Display Panel - Sublocade 300 mg Carton Label

NDC 12496-0300-1

Sublocade ®

(buprenorphine extended-release)
injection

CIII

300 mg

FOR SUBCUTANEOUS USE ONLY

WARNING: SERIOUS HARM OR DEATH
COULD RESULT IF INJECTED INTRAVENOUSLY

To be administered by a healthcare provider only.

CARTON CONTENTS: One pouch with sterile prefilled syringe containing
300 mg/1.5 mL (200 mg/mL) of buprenorphine in the ATRIGEL® Delivery
System, one oxygen absorber and one sterile 19 G 5/8" safety needle.